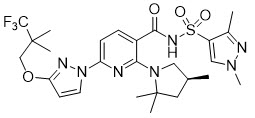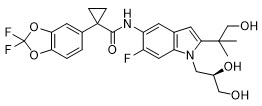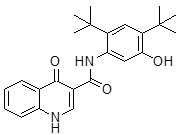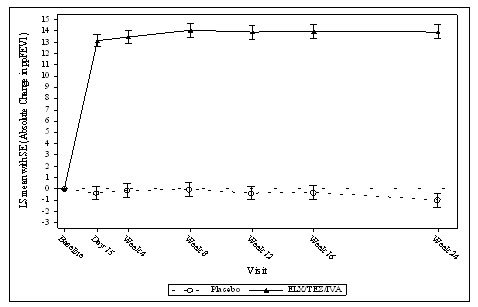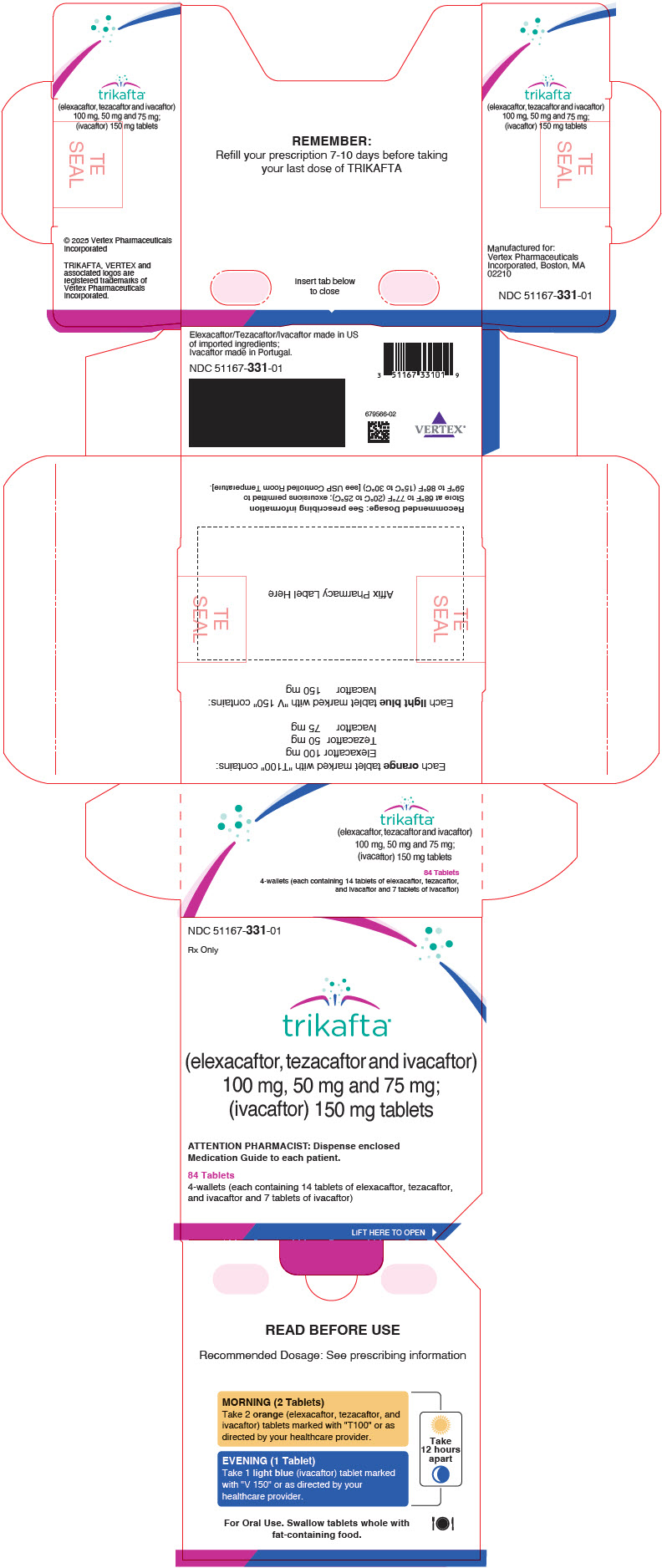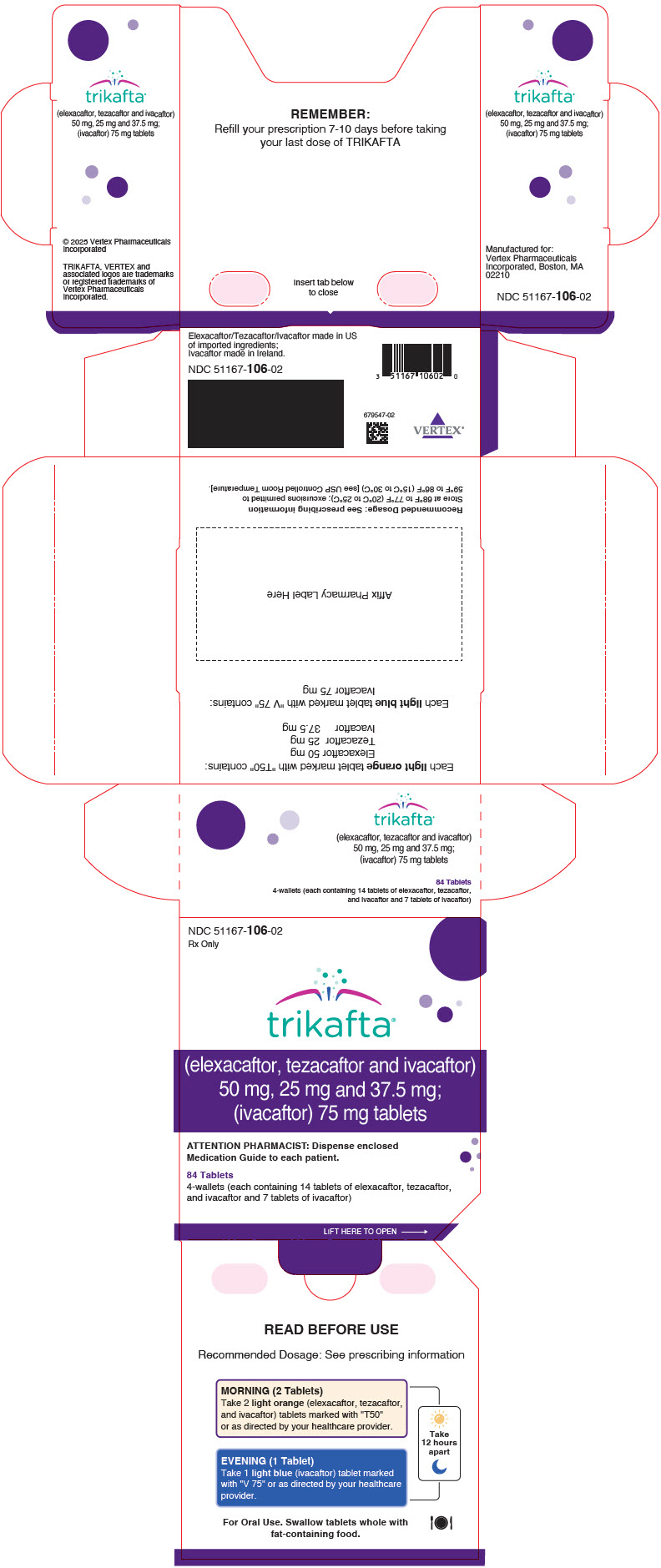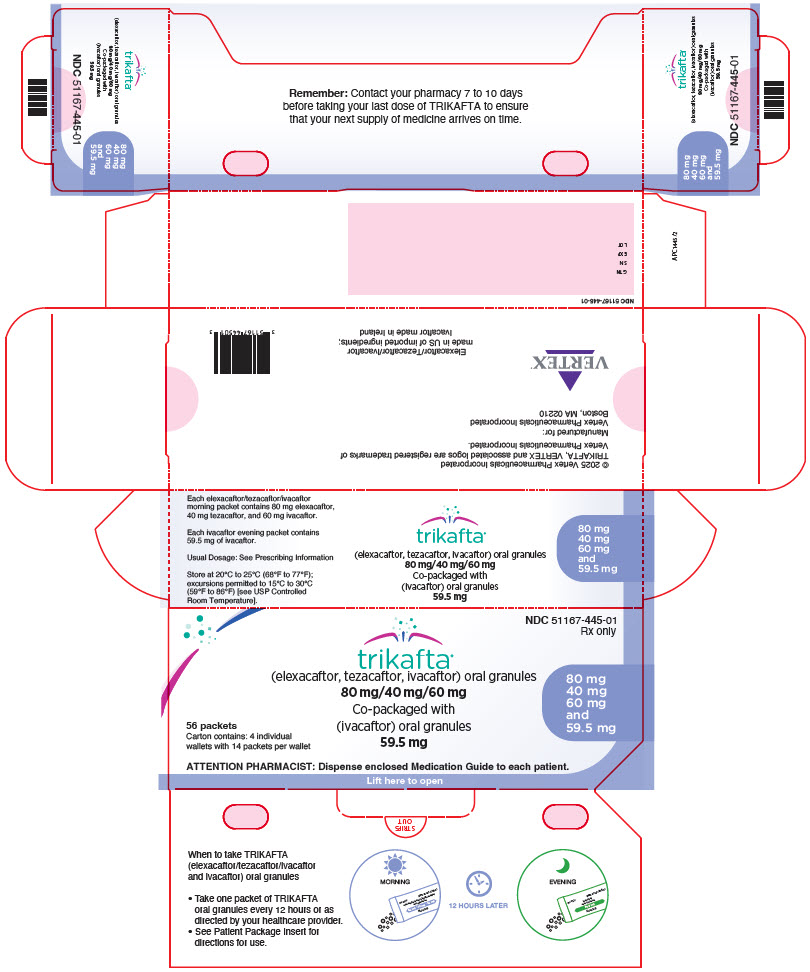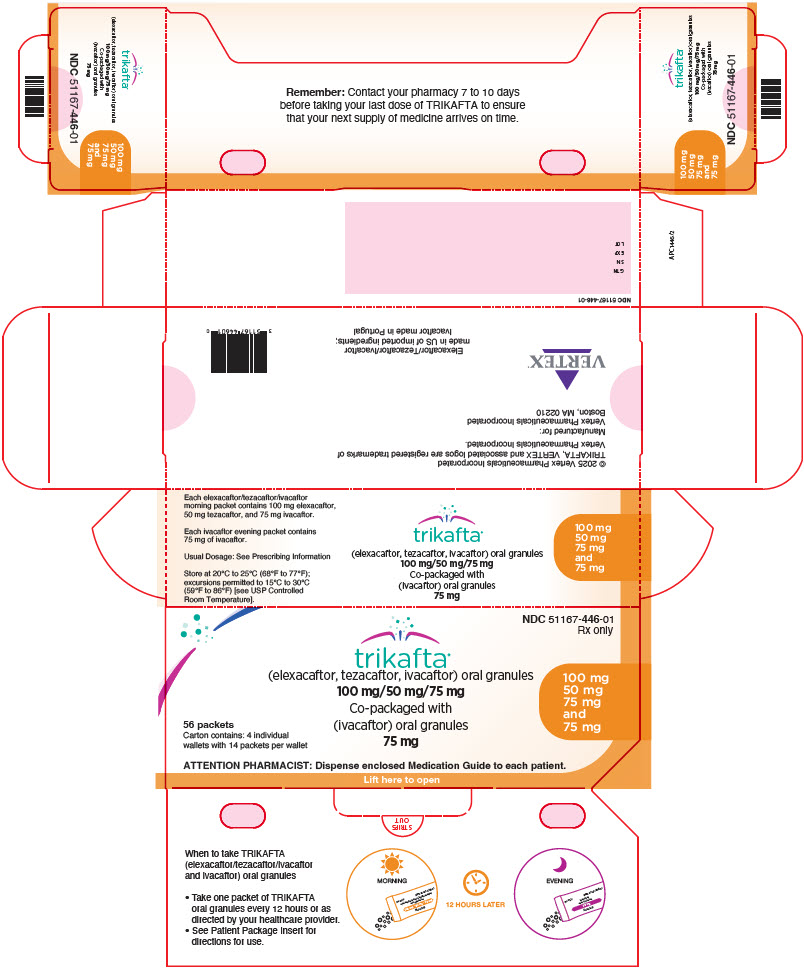 DRUG LABEL: Trikafta
NDC: 51167-331 | Form: KIT | Route: ORAL
Manufacturer: Vertex Pharmaceuticals Incorporated
Category: prescription | Type: HUMAN PRESCRIPTION DRUG LABEL
Date: 20251002

ACTIVE INGREDIENTS: Elexacaftor 100 mg/1 1; Tezacaftor 50 mg/1 1; Ivacaftor 75 mg/1 1; Ivacaftor 150 mg/1 1
INACTIVE INGREDIENTS: HYPROMELLOSE ACETATE SUCCINATE 06081224 (3 MPA.S); HYPROMELLOSE, UNSPECIFIED; sodium lauryl sulfate; croscarmellose sodium; microcrystalline cellulose; magnesium stearate; hypromellose 2910 (6 mpa.s); hydroxypropyl cellulose, unspecified; titanium dioxide; talc; ferric oxide yellow; ferric oxide red; silicon dioxide; HYPROMELLOSE ACETATE SUCCINATE 06081224 (3 MPA.S); lactose monohydrate; Magnesium stearate; microcrystalline cellulose; sodium lauryl sulfate; carnauba wax; FD&C Blue No. 2; polyethylene glycol 3350; polyvinyl alcohol, unspecified; talc; titanium dioxide; Ammonia; ferrosoferric oxide; propylene glycol; shellac; Croscarmellose sodium

HIGHLIGHTS OF PRESCRIBING INFORMATION

These highlights do not include all the information needed to use TRIKAFTA safely and effectively. See full prescribing information for TRIKAFTA.
TRIKAFTA® (elexacaftor, tezacaftor, and ivacaftor tablets; ivacaftor tablets), co-packaged for oral use
TRIKAFTA® (elexacaftor, tezacaftor, and ivacaftor oral granules; ivacaftor oral granules), co-packaged
Initial U.S. Approval: 2019

WARNING: DRUG-INDUCED LIVER INJURY AND LIVER FAILURE

See full prescribing information for complete boxed warning.

- TRIKAFTA can cause serious and potentially fatal drug-induced liver injury. Liver failure leading to transplantation and death has been reported. (5.1, 6)
- Assess liver function tests (ALT, AST, alkaline phosphatase, bilirubin) in all patients prior to initiating TRIKAFTA. (2.1, 5.1)
- Monitor liver function tests (ALT, AST, alkaline phosphatase, bilirubin) every month for the first 6 months of treatment, then every 3 months for the next 12 months, then at least annually. (2.1, 5.1)
- Interrupt TRIKAFTA for significant elevations in liver function tests or signs or symptoms of liver injury. Follow patients closely with clinical and laboratory monitoring until abnormalities resolve. (5.1)
- Resume TRIKAFTA if abnormalities resolve and only if the benefit is expected to outweigh the risk. (5.1)
- TRIKAFTA should not be used in patients with severe hepatic impairment (Child-Pugh Class C). TRIKAFTA is not recommended in patients with moderate hepatic impairment (Child-Pugh Class B). (2.3, 5.1, 8.7, 12.3)

RECENT MAJOR CHANGES

Boxed Warning | 12/2024
Indications and Usage (1) | 12/2024
Dosage and Administration (2.1) | 12/2024
Warnings and Precautions, Drug-Induced Liver Injury and Liver Failure (5.1) | 12/2024
Warnings and Precautions, Intracranial Hypertension (5.3) | 09/2025

1 INDICATIONS AND USAGE

TRIKAFTA is a combination of ivacaftor, a CFTR potentiator, tezacaftor, and elexacaftor indicated for the treatment of cystic fibrosis (CF) in patients aged 2 years and older who have at least one F508del mutation in the CFTR gene or a mutation in the CFTR gene that is responsive based on clinical and/or in vitro data.

If the patient's genotype is unknown, an FDA-cleared CF mutation test should be used to confirm the presence of at least one indicated mutation. (1)

2 DOSAGE AND ADMINISTRATION

Prior to initiating TRIKAFTA obtain liver function tests (ALT, AST, alkaline phosphatase, and bilirubin) in all patients. Monitor liver function tests every month during the first 6 months of treatment, then every 3 months during the next 12 months, then at least annually thereafter. (2.1, 5.1)

Recommended Dosage for Adult and Pediatric Patients Aged 2 Years and Older (with fat-containing food (2.2, 12.3))
Age | Weight | Morning Dose | Evening Dose
2 to less than 6 years | Less than 14 kg | One packet containing elexacaftor 80 mg/tezacaftor 40 mg/ivacaftor 60 mg oral granules | One packet containing ivacaftor 59.5 mg oral granules
2 to less than 6 years | 14 kg or more | One packet containing elexacaftor 100 mg/tezacaftor 50 mg/ivacaftor 75 mg oral granules | One packet containing ivacaftor 75 mg oral granules
6 to less than 12 years | Less than 30 kg | Two tablets, each containing elexacaftor 50 mg/tezacaftor 25 mg/ivacaftor 37.5 mg | One tablet of ivacaftor 75 mg
6 to less than 12 years | 30 kg or more | Two tablets, each containing elexacaftor 100 mg/tezacaftor 50 mg/ivacaftor 75 mg | One tablet of ivacaftor 150 mg
12 years and older | - | Two tablets, each containing elexacaftor 100 mg/tezacaftor 50 mg/ivacaftor 75 mg | One tablet of ivacaftor 150 mg

- Should not be used in patients with severe hepatic impairment. Use not recommended in patients with moderate hepatic impairment unless the benefit outweighs the risk. Reduce dose if used in patients with moderate hepatic impairment. Liver function tests should be closely monitored. (2.3, 5.1, 6, 8.7, 12.3)
- See full prescribing information for dosage modifications due to drug interactions with TRIKAFTA. (2.4, 5.5, 7.1, 12.3)

3 DOSAGE FORMS AND STRENGTHS

Tablets:

- Fixed-dose combination containing elexacaftor 50 mg, tezacaftor 25 mg and ivacaftor 37.5 mg co-packaged with ivacaftor 75 mg;
- Fixed-dose combination containing elexacaftor 100 mg, tezacaftor 50 mg, and ivacaftor 75 mg co-packaged with ivacaftor 150 mg. (3)

Oral granules:

- Unit-dose packets of elexacaftor 100 mg, tezacaftor 50 mg and ivacaftor 75 mg co-packaged with unit-dose packets of ivacaftor 75 mg;
- Unit-dose packets of elexacaftor 80 mg, tezacaftor 40 mg and ivacaftor 60 mg co-packaged with unit-dose packets of ivacaftor 59.5 mg. (3)

4 CONTRAINDICATIONS

None. (4)

5 WARNINGS AND PRECAUTIONS

- Drug-induced liver injury and liver failure: TRIKAFTA can cause serious and potentially fatal drug-induced liver injury. Assess liver function tests (ALT, AST, alkaline phosphatase, bilirubin) in all patients prior to initiating and throughout treatment with TRIKAFTA. Interrupt TRIKAFTA in the event of significant elevations in liver function tests or signs or symptoms of liver injury. TRIKAFTA should not be used in patients with severe hepatic impairment (Child-Pugh Class C). TRIKAFTA is not recommended in patients with moderate hepatic impairment (Child-Pugh Class B). (2.1, 2.3, 5.1, 6, 8.7, 12.3)
- Hypersensitivity reactions: Angioedema and anaphylaxis have been reported with TRIKAFTA in the postmarketing setting. Initiate appropriate therapy in the event of a hypersensitivity reaction. (5.2)
- Intracranial hypertension: Intracranial hypertension (IH) has been reported in the postmarketing setting with the use of TRIKAFTA. If an unusual headache or visual disturbances occur during treatment, and IH is suspected, interrupt TRIKAFTA and refer for prompt medical evaluation. (5.3)
- Use with CYP3A inducers: Concomitant use with strong CYP3A inducers (e.g., rifampin, St. John's wort) significantly decrease ivacaftor exposure and are expected to decrease elexacaftor and tezacaftor exposure, which may reduce TRIKAFTA efficacy. Therefore, concomitant use is not recommended. (5.4, 7.1, 12.3)
- Cataracts: Non-congenital lens opacities/cataracts have been reported in pediatric patients treated with ivacaftor-containing regimens. Baseline and follow-up examinations are recommended in pediatric patients initiating TRIKAFTA treatment. (5.6, 8.4)

6 ADVERSE REACTIONS

The most common adverse drug reactions to TRIKAFTA (≥5% of patients and at a frequency higher than placebo by ≥1%) were headache, upper respiratory tract infection, abdominal pain, diarrhea, rash, alanine aminotransferase increased, nasal congestion, blood creatine phosphokinase increased, aspartate aminotransferase increased, rhinorrhea, rhinitis, influenza, sinusitis, blood bilirubin increased and constipation. (6.1)

To report SUSPECTED ADVERSE REACTIONS, contact Vertex Pharmaceuticals Incorporated at 1-877-634-8789 or FDA at 1-800-FDA-1088 or www.fda.gov/medwatch.

7 DRUG INTERACTIONS

- Strong CYP3A inducers: Avoid concomitant use. (5.4, 7.1, 12.3)
- Strong or moderate CYP3A inhibitors: Reduce TRIKAFTA dosage when used concomitantly. Avoid food or drink containing grapefruit. (2.4, 5.5, 7.1, 12.3)

FULL PRESCRIBING INFORMATION

WARNING: DRUG-INDUCED LIVER INJURY AND LIVER FAILURE

TRIKAFTA can cause serious and potentially fatal drug-induced liver injury. Cases of liver failure leading to transplantation and death have been reported in patients with and without a history of liver disease taking TRIKAFTA, in both clinical trials and the postmarketing setting [see Adverse Reactions (6)]. Liver injury has been reported within the first month of therapy and up to 15 months following initiation of TRIKAFTA.

Assess liver function tests (ALT, AST, alkaline phosphatase, and bilirubin) in all patients prior to initiating TRIKAFTA. Assess liver function tests every month during the first 6 months of treatment, then every 3 months for the next 12 months, then at least annually thereafter. Consider more frequent monitoring for patients with a history of liver disease or liver function test elevations at baseline [see Dosage and Administration (2.1), Warnings and Precautions (5.1), Adverse Reactions (6), and Use in Specific Populations (8.7)].

Interrupt TRIKAFTA for significant elevations in liver function tests or in the event of signs or symptoms of liver injury. Consider referral to a hepatologist. Follow patients closely with clinical and laboratory monitoring until abnormalities resolve. If abnormalities resolve, resume treatment only if the benefit is expected to outweigh the risk. Closer monitoring is advised after resuming TRIKAFTA [see Warnings and Precautions (5.1)].

TRIKAFTA should not be used in patients with severe hepatic impairment (Child-Pugh Class C). TRIKAFTA is not recommended in patients with moderate hepatic impairment (Child-Pugh Class B). If used, use with caution at a reduced dosage and monitor patients closely [see Dosage and Administration (2.3), Warnings and Precautions (5.1), Adverse Reactions (6), Use in Specific Populations (8.7) and Clinical Pharmacology (12.3)].

1 INDICATIONS AND USAGE

TRIKAFTA is indicated for the treatment of cystic fibrosis (CF) in patients aged 2 years and older who have at least one F508del mutation in the cystic fibrosis transmembrane conductance regulator (CFTR) gene or a mutation in the CFTR gene that is responsive based on clinical and/or in vitro data (see Table 6) [see Clinical Pharmacology (12.1)].

If the patient's genotype is unknown, an FDA-cleared CF mutation test should be used to confirm the presence of at least one indicated mutation [see Clinical Pharmacology (12.1)].

2 DOSAGE AND ADMINISTRATION

2.1 Recommended Laboratory Testing Prior to TRIKAFTA Initiation and During Treatment

Prior to initiating TRIKAFTA, obtain liver function tests (ALT, AST, alkaline phosphatase, and bilirubin) for all patients. Monitor liver function tests every month during the first 6 months of treatment, then every 3 months for the next 12 months, then at least annually thereafter. Consider more frequent monitoring for patients with a history of liver disease or liver function test elevations at baseline [see Warnings and Precautions (5.1) and Use in Specific Populations (8.7)].

2.2 Recommended Dosage in Adults and Pediatric Patients Aged 2 Years and Older

Recommended dosage for adult and pediatric patients aged 2 years and older is provided in Table 1. Administer TRIKAFTA tablets (swallow the tablets whole) or oral granules orally with fat-containing food, in the morning and in the evening approximately 12 hours apart. Examples of meals or snacks that contain fat are those prepared with butter or oils or those containing eggs, peanut butter, cheeses, nuts, whole milk, or meats [see Clinical Pharmacology (12.3)].

Administer each dose of TRIKAFTA oral granules immediately before or after ingestion of fat-containing food. Mix entire contents of each packet of oral granules with one teaspoon (5 mL) of age-appropriate soft food or liquid that is at or below room temperature. Some examples of soft food or liquids include pureed fruits or vegetables, yogurt, applesauce, water, milk, or juice. Once mixed, the product should be consumed completely within one hour.

Table 1: Recommended Dosage of TRIKAFTA for Adult and Pediatric Patients Aged 2 Years and Older
Age | Weight | Oral Morning Dose | Oral Evening Dose
2 to less than 6 years | Less than 14 kg | One packet (containing elexacaftor 80 mg/tezacaftor 40 mg/ivacaftor 60 mg) oral granules | One packet (containing ivacaftor 59.5 mg) oral granules
2 to less than 6 years | 14 kg or more | One packet (containing elexacaftor 100 mg/tezacaftor 50 mg/ivacaftor 75 mg) oral granules | One packet (containing ivacaftor 75 mg) oral granules
6 to less than 12 years | Less than 30 kg | Two tablets of elexacaftor 50 mg/tezacaftor 25 mg/ivacaftor 37.5 mg (total dose of elexacaftor 100 mg/tezacaftor 50 mg/ivacaftor 75 mg) | One tablet of ivacaftor 75 mg
6 to less than 12 years | 30 kg or more | Two tablets of elexacaftor 100 mg/tezacaftor 50 mg/ivacaftor 75 mg (total dose of elexacaftor 200 mg/tezacaftor 100 mg/ivacaftor 150 mg) | One tablet of ivacaftor 150 mg
12 years and older | — | Two tablets of elexacaftor 100 mg/tezacaftor 50 mg/ivacaftor 75 mg (total dose of elexacaftor 200 mg/tezacaftor 100 mg/ivacaftor 150 mg) | One tablet of ivacaftor 150 mg

2.3 Recommended Dosage for Patients with Hepatic Impairment

- Severe Hepatic Impairment (Child-Pugh Class C): Should not be used. TRIKAFTA has not been studied in patients with severe hepatic impairment (Child-Pugh Class C), but the exposure is expected to be higher than in patients with moderate hepatic impairment [see Warnings and Precautions (5.1), Adverse Reactions (6), Use in Specific Populations (8.7) and Clinical Pharmacology (12.3)].
- Moderate Hepatic Impairment (Child-Pugh Class B): Treatment is not recommended. Use of TRIKAFTA in patients with moderate hepatic impairment should only be considered when there is a clear medical need, and the benefit outweighs the risk. If used, TRIKAFTA should be used with caution at a reduced dose (see Table 2) [see Use in Specific Populations (8.7) and Clinical Pharmacology (12.3)]. Liver function tests should be closely monitored [see Dosage and Administration (2.1) and Warnings and Precautions (5.1)]. Recommended dosage for patients with moderate hepatic impairment (Child-Pugh Class B) is provided in Table 2.

Table 2: Recommended Dosage of TRIKAFTA, if used, in Patients with Moderate Hepatic Impairment (Child-Pugh Class B)
Age | Weight | Oral Morning Dose | Oral Evening Dose
2 to less than 6 years | Less than 14 kg | Weekly dosing schedule is as follows:; - Days 1-3: One packet (containing elexacaftor 80 mg/tezacaftor 40 mg/ivacaftor 60 mg) oral granules each day - Day 4: no dose - Days 5-6: One packet (containing elexacaftor 80 mg/tezacaftor 40 mg/ivacaftor 60 mg) oral granules each day - Day 7: no dose | No evening dose of ivacaftor oral granules.
2 to less than 6 years | 14 kg or more | Weekly dosing schedule is as follows:; - Days 1-3: One packet (containing elexacaftor 100 mg/tezacaftor 50 mg/ivacaftor 75 mg) oral granules each day - Day 4: no dose - Days 5-6: One packet (containing elexacaftor 100 mg/tezacaftor 50 mg/ivacaftor 75 mg) oral granules each day - Day 7: no dose | No evening dose of ivacaftor oral granules.
6 to less than 12 years | Less than 30 kg | Alternating daily dosing schedule is as follows:; - Day 1: Two tablets of elexacaftor 50 mg/tezacaftor 25 mg/ivacaftor 37.5 mg (total dose of elexacaftor 100 mg/tezacaftor 50 mg/ivacaftor 75 mg) - Day 2: One tablet of elexacaftor 50 mg/tezacaftor 25 mg/ivacaftor 37.5 mg | No evening ivacaftor tablet dose.
6 to less than 12 years | 30 kg or more | Alternating daily dosing schedule is as follows:; - Day 1: Two tablets of elexacaftor 100 mg/tezacaftor 50 mg/ivacaftor 75 mg (total dose of elexacaftor 200 mg/tezacaftor 100 mg/ivacaftor 150 mg) - Day 2: One tablet elexacaftor 100 mg/tezacaftor 50 mg/ivacaftor 75 mg | No evening ivacaftor tablet dose.
12 years and older | — | Alternating daily dosing schedule is as follows:; - Day 1: Two tablets of elexacaftor 100 mg/tezacaftor 50 mg/ivacaftor 75 mg (total dose of elexacaftor 200 mg/tezacaftor 100 mg/ivacaftor 150 mg) - Day 2: One tablet elexacaftor 100 mg/tezacaftor 50 mg/ivacaftor 75 mg | No evening ivacaftor tablet dose.

- Mild Hepatic Impairment (Child-Pugh Class A): No dose adjustment is recommended [see Use in Specific Populations (8.7) and Clinical Pharmacology (12.3)]. See Table 1 for recommended dosage of TRIKAFTA. Liver function tests should be closely monitored [see Dosage and Administration (2.1) and Warnings and Precautions (5.1)].

2.4 Dosage Modification for Patients Taking Drugs that are CYP3A Inhibitors

Table 3 describes the recommended dosage modification for TRIKAFTA when used concomitantly with strong (e.g., ketoconazole, itraconazole, posaconazole, voriconazole, telithromycin, and clarithromycin) or moderate (e.g., fluconazole, erythromycin) CYP3A inhibitors. Administer TRIKAFTA orally with fat-containing food [see Dosage and Administration (2.2)]. Avoid food or drink containing grapefruit during TRIKAFTA treatment [see Warnings and Precautions (5.5), Drug Interactions (7.1) and Clinical Pharmacology (12.3)].

Table 3: Dosage Modification for Concomitant Use of TRIKAFTA with Moderate and Strong CYP3A Inhibitors
Age | Weight | Moderate CYP3A Inhibitors | Strong CYP3A Inhibitors
2 to less than 6 years | Less than 14 kg | Alternating daily dosing schedule is as follows:; - Day 1: One packet (containing elexacaftor 80 mg/tezacaftor 40 mg/ivacaftor 60 mg) in the morning - Day 2: One packet (containing ivacaftor 59.5 mg) oral granules in the morning; No evening packet of ivacaftor oral granules. | One packet (containing elexacaftor 80 mg/tezacaftor 40 mg/ivacaftor 60 mg) in the morning twice a week, approximately 3 to 4 days apart. No evening packet of ivacaftor oral granules.
2 to less than 6 years | 14 kg or more | Alternating daily dosing schedule is as follows:; - Day 1: One packet (containing elexacaftor 100 mg/tezacaftor 50 mg/ivacaftor 75 mg) in the morning - Day 2: One packet (containing ivacaftor 75 mg) oral granules in the morning; No evening packet of ivacaftor oral granules. | One packet (containing elexacaftor 100 mg/tezacaftor 50 mg/ivacaftor 75 mg) in the morning twice a week, approximately 3 to 4 days apart. No evening packet of ivacaftor oral granules.
6 to less than 12 years | Less than 30 kg | Alternating daily dosing schedule is as follows:; - Day 1: Two tablets of elexacaftor 50 mg/tezacaftor 25 mg/ivacaftor 37.5 mg (total dose of elexacaftor 100 mg/tezacaftor 50 mg/ivacaftor 75 mg) in the morning - Day 2: One tablet of ivacaftor 75 mg in the morning; No evening ivacaftor tablet dose. | Two tablets of elexacaftor 50 mg/tezacaftor 25 mg/ivacaftor 37.5 mg (total dose of elexacaftor 100 mg/tezacaftor 50 mg/ivacaftor 75 mg) in the morning twice a week, approximately 3 to 4 days apart. No evening ivacaftor tablet dose.
6 to less than 12 years | 30 kg or more | Alternating daily dosing schedule is as follows:; - Day 1: Two tablets elexacaftor 100 mg/tezacaftor 50 mg/ivacaftor 75 mg (total dose of elexacaftor 200 mg/tezacaftor100 mg/ivacaftor 150 mg) in the morning - Day 2: One tablet of ivacaftor 150 mg in the morning; No evening ivacaftor tablet dose. | Two tablets elexacaftor 100 mg/tezacaftor 50 mg/ivacaftor 75 mg (total dose of elexacaftor 200 mg/tezacaftor 100 mg/ivacaftor 150 mg) in the morning twice a week, approximately 3 to 4 days apart. No evening ivacaftor tablet dose.
12 years and older |  | Alternating daily dosing schedule is as follows:; - Day 1: Two tablets elexacaftor 100 mg/tezacaftor 50 mg/ivacaftor 75 mg (total dose of elexacaftor 200 mg/tezacaftor 100 mg/ivacaftor 150 mg) in the morning - Day 2: One tablet of ivacaftor 150 mg in the morning; No evening ivacaftor tablet dose. | Two tablets elexacaftor 100 mg/tezacaftor 50 mg/ivacaftor 75 mg (total dose of elexacaftor 200 mg/tezacaftor 100 mg/ivacaftor 150 mg) in the morning twice a week, approximately 3 to 4 days apart. No evening ivacaftor tablet dose.

2.5 Recommendations Regarding Missed Dose(s)

If 6 hours or less have passed since the missed morning or evening dose, the patient should take the missed dose as soon as possible and continue on the original schedule.

If more than 6 hours have passed since:

- the missed morning dose, the patient should take the missed dose as soon as possible and should not take the evening dose. The next scheduled morning dose should be taken at the usual time.
- the missed evening dose, the patient should not take the missed dose. The next scheduled morning dose should be taken at the usual time.

Morning and evening doses should not be taken at the same time.

3 DOSAGE FORMS AND STRENGTHS

Tablets:

Fixed-dose combination containing elexacaftor 50 mg, tezacaftor 25 mg, and ivacaftor 37.5 mg co-packaged with ivacaftor 75 mg:

- Elexacaftor, tezacaftor and ivacaftor tablets are light orange, oblong-shaped and debossed with "T50" on one side and plain on the other
- Ivacaftor tablets are light blue, oblong-shaped, and printed with "V 75" in black ink on one side and plain on the other

Fixed-dose combination containing elexacaftor 100 mg, tezacaftor 50 mg, and ivacaftor 75 mg co-packaged with ivacaftor 150 mg:

- Elexacaftor, tezacaftor and ivacaftor tablets are orange, oblong-shaped and debossed with "T100" on one side and plain on the other
- Ivacaftor tablets are light blue, oblong-shaped, and printed with "V 150" in black ink on one side and plain on the other

Oral Granules:

Fixed-dose combination oral granules containing elexacaftor 100 mg, tezacaftor 50 mg, and ivacaftor 75 mg co-packaged with ivacaftor 75 mg oral granules:

- Elexacaftor, tezacaftor, and ivacaftor oral granules are white to off-white, sweetened, unflavored granules approximately 2 mm in diameter contained in a white and orange unit-dose packet
- Ivacaftor oral granules are white to off-white, sweetened, unflavored granules approximately 2 mm in diameter contained in a white and pink unit-dose packet

Fixed-dose combination oral granules containing elexacaftor 80 mg, tezacaftor 40 mg, and ivacaftor 60 mg co-packaged with ivacaftor 59.5 mg oral granules:

- Elexacaftor, tezacaftor, and ivacaftor oral granules are white to off-white, sweetened, unflavored granules approximately 2 mm in diameter contained in a white and blue unit-dose packet
- Ivacaftor oral granules are white to off-white, sweetened, unflavored granules approximately 2 mm in diameter contained in a white and green unit-dose packet

4 CONTRAINDICATIONS

None.

5 WARNINGS AND PRECAUTIONS

5.1 Drug-Induced Liver Injury and Liver Failure

TRIKAFTA can cause serious and potentially fatal drug-induced liver injury. Cases of liver failure leading to transplantation and death have been reported in patients with and without a history of liver disease taking TRIKAFTA, in both clinical trials and the postmarketing setting [see Adverse Reactions (6)]. Liver injury has been reported within the first month of therapy and up to 15 months following initiation of TRIKAFTA.

Assess liver function tests (ALT, AST, alkaline phosphatase, and bilirubin) in all patients prior to initiating TRIKAFTA. Assess liver function tests every month during the first 6 months of treatment, then every 3 months for the next 12 months, then at least annually thereafter. Consider more frequent monitoring for patients with a history of liver disease or liver function test elevations at baseline [see Dosage and Administration (2.1), Adverse Reactions (6), and Use in Specific Populations (8.7)].

Interrupt TRIKAFTA in the event of signs or symptoms of liver injury. These may include:

- Significant elevations in liver function tests (e.g., ALT or AST >5 × the upper limit of normal (ULN) or ALT or AST >3 × ULN with bilirubin >2 × ULN)
- Clinical symptoms suggestive of liver injury (e.g., jaundice, right upper quadrant pain, nausea, vomiting, altered mental status, ascites).

Consider referral to a hepatologist and follow patients closely with clinical and laboratory monitoring until abnormalities resolve. If abnormalities resolve and if the benefit is expected to outweigh the risk, resume TRIKAFTA treatment with close monitoring.

TRIKAFTA should not be used in patients with severe hepatic impairment (Child-Pugh Class C). TRIKAFTA is not recommended in patients with moderate hepatic impairment (Child-Pugh Class B) and should only be considered when there is a clear medical need, and the benefit outweighs the risk. If used, use with caution at a reduced dosage and monitor patients closely [see Dosage and Administration (2.3), Use in Specific Populations (8.7) and Clinical Pharmacology (12.3)].

5.2 Hypersensitivity Reactions, Including Anaphylaxis

Hypersensitivity reactions, including cases of angioedema and anaphylaxis, have been reported in the postmarketing setting [see Adverse Reactions (6.2)]. If signs or symptoms of serious hypersensitivity reactions develop during treatment, discontinue TRIKAFTA and institute appropriate therapy. Consider the benefits and risks for the individual patient to determine whether to resume treatment with TRIKAFTA.

5.3 Intracranial Hypertension

Cases of intracranial hypertension (IH) have been reported in the postmarketing setting with the use of TRIKAFTA [see Adverse Reactions (6.2)]. Clinical manifestations of IH include headache, blurred vision, diplopia, and potential vision loss; papilledema can be found on fundoscopy. If an unusual headache or visual disturbances occur during treatment, and IH is suspected, interrupt TRIKAFTA and refer for prompt medical evaluation. Consider the benefits and risks for the individual patient to determine whether to resume treatment with TRIKAFTA. Patients should be monitored until IH resolution and for recurrence. Patients with elevated vitamin A levels may be at increased risk.

5.4 Concomitant Use with CYP3A Inducers

Exposure to ivacaftor is significantly decreased and exposure to elexacaftor and tezacaftor are expected to decrease by the concomitant use of strong CYP3A inducers, which may reduce the therapeutic effectiveness of TRIKAFTA. Therefore, concomitant use with strong CYP3A inducers is not recommended [see Drug Interactions (7.1) and Clinical Pharmacology (12.3)].

5.5 Concomitant Use with CYP3A Inhibitors

Exposure to elexacaftor, tezacaftor and ivacaftor are increased when used concomitantly with strong or moderate CYP3A inhibitors. Therefore, the dose of TRIKAFTA should be reduced when used concomitantly with moderate or strong CYP3A inhibitors [see Dosage and Administration (2.4), Drug Interactions (7.1) and Clinical Pharmacology (12.3)].

5.6 Cataracts

Cases of non-congenital lens opacities have been reported in pediatric patients treated with ivacaftor-containing regimens. Although other risk factors were present in some cases (such as corticosteroid use, exposure to radiation), a possible risk attributable to treatment with ivacaftor cannot be excluded. Baseline and follow-up ophthalmological examinations are recommended in pediatric patients initiating treatment with TRIKAFTA [see Use in Specific Populations (8.4)].

6 ADVERSE REACTIONS

The following clinically significant adverse reactions are discussed in greater detail in other sections of the labeling:

- Drug-Induced Liver Injury and Liver Failure [see Warnings and Precautions (5.1)]
- Hypersensitivity Reactions, Including Anaphylaxis [see Warnings and Precautions (5.2)]
- Intracranial Hypertension [see Warnings and Precautions (5.3)]
- Cataracts [see Warnings and Precautions (5.6)]

6.1 Clinical Trials Experience

Because clinical trials are conducted under widely varying conditions, adverse reaction rates observed in the clinical trials of a drug cannot be directly compared to rates in the clinical trials of another drug and may not reflect the rates observed in clinical practice.

Patients with Cystic Fibrosis with at Least One F508del Mutation

The safety profile of TRIKAFTA in patients with CF with at least one F508del mutation is based on data from 510 patients aged 12 years and older in two double-blind, controlled trials of 24 weeks and 4 weeks treatment duration (Trials 1 and 2, respectively). Eligible patients were also able to participate in an open-label extension safety study (up to 96 weeks of TRIKAFTA). In the two controlled trials, a total of 257 patients aged 12 years and older received at least one dose of TRIKAFTA.

In Trial 1, the proportion of patients who discontinued study drug prematurely due to adverse events was 1% for TRIKAFTA-treated patients and 0% for placebo-treated patients.

In Trial 1, serious adverse reactions that occurred more frequently in TRIKAFTA-treated patients compared to placebo were rash (1% vs <1%) and influenza (1% vs 0%). There were no deaths.

Table 4 shows adverse reactions occurring in ≥5% of TRIKAFTA-treated patients and higher than placebo by ≥1% in the 24-week, placebo-controlled, parallel-group trial (Trial 1).

Table 4: Adverse Reactions Occurring in ≥5% of TRIKAFTA-Treated Patients and Higher than Placebo by ≥1% in Trial 1
Adverse Reactions | TRIKAFTA N=202 n (%) | Placebo N=201 n (%)
Headache | 35 (17) | 30 (15)
Upper respiratory tract infection [Includes upper respiratory tract infection and viral upper respiratory tract infection.] | 32 (16) | 25 (12)
Abdominal pain [Includes abdominal pain, abdominal pain upper, abdominal pain lower.] | 29 (14) | 18 (9)
Diarrhea | 26 (13) | 14 (7)
Rash [Includes rash, rash generalized, rash erythematous, rash macular, rash pruritic.] | 21 (10) | 10 (5)
Alanine aminotransferase increased | 20 (10) | 7 (3)
Nasal congestion | 19 (9) | 15 (7)
Blood creatine phosphokinase increased | 19 (9) | 9 (4)
Aspartate aminotransferase increased | 19 (9) | 4 (2)
Rhinorrhea | 17 (8) | 6 (3)
Rhinitis | 15 (7) | 11 (5)
Influenza | 14 (7) | 3 (1)
Sinusitis | 11 (5) | 8 (4)
Blood bilirubin increased | 10 (5) | 2 (1)

Additional adverse reactions that occurred in TRIKAFTA-treated patients at a frequency of 2% to <5% and higher than placebo by ≥1% include the following: flatulence, abdominal distension, conjunctivitis, pharyngitis, respiratory tract infection, tonsillitis, urinary tract infection, c-reactive protein increased, hypoglycemia, dizziness, dysmenorrhea, acne, eczema and pruritus.

In addition, the following clinical trials have also been conducted [see Use in Specific Populations (8.4), Clinical Pharmacology (12.3) and Clinical Studies (14)]:

- a 24-week, open-label trial in 66 patients with CF aged 6 to less than 12 years who were either homozygous for the F508del mutation or heterozygous for the F508del mutation, and a mutation on the second allele that results in either no CFTR protein or a CFTR protein that is not responsive to ivacaftor and tezacaftor/ivacaftor (Trial 3).
- a 24-week, open-label trial in 75 patients with CF aged 2 to less than 6 years. Patients who had at least one F508del mutation or a mutation known to be responsive to TRIKAFTA were eligible for the study (Trial 4).

The safety profile for the CF patients enrolled in Trials 2, 3, and 4 was consistent to that observed in Trial 1.

Patients with Cystic Fibrosis with at Least One Qualifying Non-F508del Mutation

The safety of TRIKAFTA in patients with CF with at least one non-F508del mutation is based on data from 307 patients aged 6 years and older with at least one qualifying non-F508del CFTR mutation that was TRIKAFTA-responsive. Trial 5 was a randomized, double blind, placebo-controlled trial for a 24-week treatment duration in which 205 patients received at least one dose of TRIKAFTA. Eligible patients were also able to participate in an open-label extension safety study.

In Trial 5, the proportion of patients who discontinued study drug prematurely due to adverse reactions was 2% for TRIKAFTA-treated patients and 0% for placebo-treated patients.

Table 5 shows adverse reactions occurring in ≥5% of TRIKAFTA-treated patients and higher than placebo by ≥1% in the 24-week, placebo-controlled, parallel-group trial (Trial 5).

Table 5: Adverse Reactions Occurring in ≥5% of TRIKAFTA-Treated Patients and Higher than Placebo by ≥1% in Trial 5
Adverse Reactions | TRIKAFTA N=205 n (%) | Placebo N=102 n (%)
Rash [Includes rash, rash maculo-papular, rash erythematous, rash papular] | 48 (23) | 2 (2)
Headache | 37 (18) | 13 (13)
Diarrhea | 26 (13) | 10 (10)
Rhinitis | 20 (10) | 6 (6)
Influenza | 18 (9) | 2 (2)
Constipation | 15 (7) | 4 (4)

Specific Adverse Reactions

Liver Function Test Elevations

In Trial 1, the incidence of maximum transaminase (ALT or AST) >8, >5, or >3 × ULN was 1%, 2%, and 8% in TRIKAFTA-treated patients and 1%, 1%, and 5% in placebo-treated patients. The incidence of adverse reactions of transaminase elevations (AST and/or ALT) was 11% in TRIKAFTA-treated patients and 4% in placebo-treated patients.

In Trial 1, the incidence of maximum total bilirubin elevation >2 × ULN was 4% in TRIKAFTA-treated patients and <1% in placebo-treated patients. Maximum indirect and direct bilirubin elevations >1.5 × ULN occurred in 11% and 3% of TRIKAFTA-treated patients, respectively. No TRIKAFTA-treated patients developed maximum direct bilirubin elevation >2 × ULN.

During Trial 3, in patients aged 6 to less than 12 years, the incidence of maximum transaminase (ALT or AST) >8, >5, and >3 × ULN were 0%, 1.5%, and 10.6%, respectively. No TRIKAFTA-treated patients had transaminase elevation >3 × ULN associated with elevated total bilirubin >2 × ULN or discontinued treatment due to transaminase elevations.

During Trial 4 in patients aged 2 to less than 6 years, the incidence of maximum transaminase (ALT or AST) >8, >5, and >3 × ULN were 1.3%, 2.7%, and 8.0%, respectively. No TRIKAFTA-treated patients had transaminase elevation >3 × ULN associated with elevated total bilirubin >2 × ULN. One patient required treatment interruption during Trial 4 and later discontinued TRIKAFTA during the open label extension due to transaminase elevations.

In Trial 5, the incidence of maximum transaminase (ALT or AST) >8, >5, and >3 × ULN were 2.0%, 2.0%, and 6.3%, respectively, and led to treatment discontinuation in 0.5% and treatment interruptions in 1.5% of TRIKAFTA-treated patients. There were no transaminase elevations >3 × ULN in placebo-treated patients.

Rash

In Trial 1, the overall incidence of rash was 10% in TRIKAFTA-treated and 5% in placebo-treated patients (see Table 4). The incidence of rash was higher in female TRIKAFTA-treated patients (16%) than in male TRIKAFTA-treated patients (5%).

In Trial 5, the overall incidence of rash was 23% in TRIKAFTA-treated and 2% in placebo-treated patients (see Table 5). The incidence of rash was higher in female TRIKAFTA-treated patients (27%) than in male TRIKAFTA-treated patients (20%).

A role of hormonal contraceptives in the occurrence of rash cannot be excluded [see Drug Interactions (7.3)].

Increased Creatine Phosphokinase

In Trial 1, the incidence of maximum creatine phosphokinase elevation >5 × ULN was 10% in TRIKAFTA-treated and 5% in placebo-treated patients. Among the TRIKAFTA-treated patients with creatine phosphokinase elevation >5 × ULN, 14% (3/21) required treatment interruption and none discontinued treatment.

In Trial 5, the incidence of maximum creatine phosphokinase elevation >5 × ULN was 5.4% (11/205) in TRIKAFTA-treated patients and 1% (1/102) in placebo-treated patients. The incidence of maximum creatine phosphokinase elevation >10 × ULN was 2.4% (5/205) in TRIKAFTA-treated patients and 1% (1/102) in placebo-treated patients. There were no interruptions or discontinuations among the TRIKAFTA-treated patients with creatine phosphokinase elevation >5 × ULN. Among the TRIKAFTA-treated patients with creatine phosphokinase elevation > 10 × ULN, two patients, who had exercised within the preceding 72 hours, developed rhabdomyolysis without evidence of renal involvement resulting in treatment interruption in 1 patient.

Increased Blood Pressure

In Trial 1, the maximum increase from baseline in mean systolic and diastolic blood pressure was 3.5 mmHg and 1.9 mmHg, respectively for TRIKAFTA-treated patients (baseline: 113 mmHg systolic and 69 mmHg diastolic) and 0.9 mmHg and 0.5 mmHg, respectively for placebo-treated patients (baseline: 114 mmHg systolic and 70 mmHg diastolic).

The proportion of patients who had systolic blood pressure >140 mmHg and 10 mmHg increase from baseline on at least two occasions was 4% in TRIKAFTA-treated patients and 1% in placebo-treated patients. The proportion of patients who had diastolic blood pressure >90 mmHg and 5 mmHg increase from baseline on at least two occasions was 1% in TRIKAFTA-treated patients and 2% in placebo-treated patients.

With the exception of sex differences in rash, the safety profile of TRIKAFTA was generally similar across all subgroups of patients, including analysis by age, sex, baseline percent predicted FEV1 (ppFEV1) and geographic regions.

6.2 Postmarketing Experience

The following adverse reactions have been identified during postapproval use of TRIKAFTA. Because these reactions are reported voluntarily from a population of uncertain size, it is not always possible to reliably estimate their frequency or establish a causal relationship to drug exposure.

Hepatobiliary: liver injury, fatal liver failure, liver transplantation

Immune System Disorders: anaphylaxis, angioedema

Nervous System Disorders: intracranial hypertension

7 DRUG INTERACTIONS

7.1 Effect of Other Drugs and Grapefruit on TRIKAFTA

Strong CYP3A Inducers

Concomitant use of TRIKAFTA with strong CYP3A inducers is not recommended. Elexacaftor, tezacaftor and ivacaftor are substrates of CYP3A (ivacaftor is a sensitive substrate of CYP3A). Concomitant use of CYP3A inducers may result in reduced exposures and thus reduced TRIKAFTA efficacy [see Warnings and Precautions (5.4)]. Concomitant use of ivacaftor with rifampin, a strong CYP3A inducer, significantly decreased ivacaftor area under the curve (AUC) by 89%. Elexacaftor and tezacaftor exposures are expected to decrease during concomitant use with strong CYP3A inducers [see Clinical Pharmacology (12.3)].

Examples of strong CYP3A inducers include:

- rifampin, rifabutin, phenobarbital, carbamazepine, phenytoin and St. John's wort (Hypericum perforatum)

Strong or Moderate CYP3A Inhibitors

The dosage of TRIKAFTA should be reduced when used concomitantly with strong CYP3A inhibitors [see Dosage and Administration (2.4) and Warnings and Precautions (5.5)]. Concomitant use with itraconazole, a strong CYP3A inhibitor, increased elexacaftor AUC by 2.8-fold and tezacaftor AUC by 4.0- to 4.5-fold. When used concomitantly with itraconazole and ketoconazole, ivacaftor AUC increased by 15.6-fold and 8.5-fold, respectively [see Clinical Pharmacology (12.3)].

Examples of strong CYP3A inhibitors include:

- ketoconazole, itraconazole, posaconazole and voriconazole
- telithromycin and clarithromycin

The dosage of TRIKAFTA should be reduced when used concomitantly with moderate CYP3A inhibitors [see Dosage and Administration (2.4) and Warnings and Precautions (5.5)]. Simulations indicated that concomitant use with moderate CYP3A inhibitors may increase elexacaftor and tezacaftor AUC by approximately 1.9- to 2.3-fold and 2.1-fold, respectively. Concomitant use of fluconazole increased ivacaftor AUC by 2.9-fold [see Clinical Pharmacology (12.3)].

Examples of moderate CYP3A inhibitors include:

- fluconazole
- erythromycin

Grapefruit

Concomitant use of TRIKAFTA with grapefruit juice, which contains one or more components that moderately inhibit CYP3A, may increase exposure of elexacaftor, tezacaftor and ivacaftor; therefore, food or drink containing grapefruit should be avoided during treatment with TRIKAFTA [see Dosage and Administration (2.4)].

7.2 Effect of TRIKAFTA on Other Drugs

CYP2C9 Substrates

Ivacaftor may inhibit CYP2C9; therefore, monitoring of the international normalized ratio (INR) during concomitant use of TRIKAFTA with warfarin is recommended. Other medicinal products for which exposure may be increased by TRIKAFTA include glimepiride and glipizide; these medicinal products should be used with caution [see Clinical Pharmacology (12.3)].

Transporters

Concomitant use of ivacaftor or tezacaftor/ivacaftor with digoxin, a sensitive P-gp substrate, increased digoxin AUC by 1.3-fold, consistent with weak inhibition of P-gp by ivacaftor. Administration of TRIKAFTA may increase systemic exposure of medicinal products that are sensitive substrates of P-gp, which may increase or prolong their therapeutic effect and adverse reactions. When used concomitantly with digoxin or other substrates of P-gp with a narrow therapeutic index such as cyclosporine, everolimus, sirolimus and tacrolimus, caution and appropriate monitoring should be used [see Clinical Pharmacology (12.3)].

Elexacaftor and M23-ELX inhibit uptake by OATP1B1 and OATP1B3 in vitro. Concomitant use of TRIKAFTA may increase exposures of medicinal products that are substrates of these transporters, such as statins, glyburide, nateglinide and repaglinide. When used concomitantly with substrates of OATP1B1 or OATP1B3, caution and appropriate monitoring should be used [see Clinical Pharmacology (12.3)]. Bilirubin is an OATP1B1 and OATP1B3 substrate.

7.3 Drugs with No Clinically Significant Interactions with TRIKAFTA

Ciprofloxacin

Ciprofloxacin had no clinically relevant effect on the exposure of tezacaftor or ivacaftor and is not expected to affect the exposure of elexacaftor. Therefore, no dose adjustment is necessary during concomitant administration of TRIKAFTA with ciprofloxacin [see Clinical Pharmacology (12.3)].

Hormonal Contraceptives

TRIKAFTA has been studied with ethinyl estradiol/levonorgestrel and was found to have no clinically relevant effect on the exposures of the oral contraceptive. TRIKAFTA is not expected to have an impact on the efficacy of oral contraceptives.

Hormonal contraceptives may play a role in the occurrence of rash and cannot be excluded [see Adverse Reactions (6.1)]. For patients with CF taking hormonal contraceptives who develop rash, consider interrupting TRIKAFTA and hormonal contraceptives. Following the resolution of rash, consider resuming TRIKAFTA without the hormonal contraceptives. If rash does not recur, resumption of hormonal contraceptives can be considered.

8 USE IN SPECIFIC POPULATIONS

8.1 Pregnancy

Risk Summary

There are limited and incomplete human data from clinical trials on the use of TRIKAFTA or its individual components, elexacaftor, tezacaftor and ivacaftor, in pregnant women to inform a drug-associated risk. Although there are no animal reproduction studies with the concomitant administration of elexacaftor, tezacaftor and ivacaftor, separate reproductive and developmental studies were conducted with each active component of TRIKAFTA in pregnant rats and rabbits.

In animal embryo fetal development (EFD) studies oral administration of elexacaftor to pregnant rats and rabbits during organogenesis demonstrated no adverse developmental effects at doses that produced maternal exposures up to approximately 2 times the exposure at the maximum recommended human dose (MRHD) in rats and 4 times the MRHD in rabbits [based on summed AUCs of elexacaftor and its metabolite (for rat) and AUC of elexacaftor (for rabbit)]. Oral administration of tezacaftor to pregnant rats and rabbits during organogenesis demonstrated no adverse developmental effects at doses that produced maternal exposures up to approximately 3 times the exposure at the MRHD in rats and 0.2 times the MRHD in rabbits (based on summed AUCs of tezacaftor and M1-TEZ). Oral administration of ivacaftor to pregnant rats and rabbits during organogenesis demonstrated no adverse developmental effects at doses that produced maternal exposures up to approximately 5 and 14 times the exposure at the MRHD, respectively [based on summed AUCs of ivacaftor and its metabolites (for rat) and AUC of ivacaftor (for rabbit)]. No adverse developmental effects were observed after oral administration of elexacaftor, tezacaftor or ivacaftor to pregnant rats from the period of organogenesis through lactation at doses that produced maternal exposures approximately 1 time, approximately 1 time and 3 times the exposures at the MRHD, respectively [based on summed AUCs of parent and metabolite(s)] (see Data).

The background risk of major birth defects and miscarriage for the indicated population is unknown. In the U.S. general population, the estimated background risk of major birth defects and miscarriage in clinically recognized pregnancies is 2% to 4% and 15% to 20%, respectively.

Data

Animal Data

Elexacaftor

In an EFD study, pregnant rats were administered oral doses of elexacaftor at 15, 25, and 40 mg/kg/day during the period of organogenesis from gestation Days 6-17. Elexacaftor did not cause adverse developmental outcomes at exposures up to 9 times the MRHD (based on summed AUCs for elexacaftor and its metabolite at maternal doses up to 40 mg/kg/day). Lower mean fetal body weights were observed at doses ≥25 mg/kg/day that produced maternal exposures ≥4 times the MRHD. Maternal toxicity was observed at 40 mg/kg/day (9 times the MRHD). In an EFD study, pregnant rabbits were administered oral doses of elexacaftor at 50, 100, or 125 mg/kg/day during the period of organogenesis from gestation Days 7-20. Elexacaftor was not teratogenic at exposures up to 4 times the MRHD (based on AUC of elexacaftor at maternal doses up to 125 mg/kg/day). Maternal toxicity was observed at 125 mg/kg/day (4 times the MRHD). In a pre- and postnatal development (PPND), pregnant rats were administered elexacaftor at oral doses of 5, 7.5, and 10 mg/kg/day from gestation Day 6 through lactation Day 18. Elexacaftor did not cause adverse developmental outcomes in pups at maternal doses up to 10 mg/kg/day (approximately 1 time the MRHD based on summed AUCs of elexacaftor and its metabolite). Placental transfer of elexacaftor was observed in pregnant rats.

Tezacaftor

In an EFD study, pregnant rats were administered tezacaftor at oral doses of 25, 50, or 100 mg/kg/day during the period of organogenesis from gestation Days 6-17. Tezacaftor did not cause adverse developmental effects at exposures up to 3 times the MRHD (based on summed AUCs of tezacaftor and M1-TEZ). Maternal toxicity in rats was observed at greater than or equal to 50 mg/kg/day (approximately greater than or equal to 1 time the MRHD). In an EFD study, pregnant rabbits were administered tezacaftor at oral doses of 10, 25, or 50 mg/kg/day during the period of organogenesis from gestation Days 7-20. Tezacaftor did not affect fetal developmental outcomes at exposures up to 0.2 times the MRHD (based on summed AUCs of tezacaftor and M1-TEZ). Lower fetal body weights were observed in rabbits at a maternally toxic dose that produced exposures approximately 1 time the MRHD (based on summed AUCs of tezacaftor and M1-TEZ at a maternal dose of 50 mg/kg/day). In a PPND study, pregnant rats were administered tezacaftor at oral doses of 25, 50, or 100 mg/kg/day from gestation Day 6 through lactation Day 18. Tezacaftor had no adverse developmental effects on pups at an exposure of approximately 1 time the MRHD (based on summed AUCs for tezacaftor and M1-TEZ at a maternal dose of 25 mg/kg/day). Decreased fetal body weights and early developmental delays in pinna detachment, eye opening, and righting reflex occurred at a maternally toxic dose (based on maternal weight loss) that produced exposures approximately 2 times the exposure at the MRHD (based on summed AUCs for tezacaftor and M1-TEZ). Placental transfer of tezacaftor was observed in pregnant rats.

Ivacaftor

In an EFD study, pregnant rats were administered ivacaftor at oral doses of 50, 100, or 200 mg/kg/day during the period of organogenesis from gestation Days 7-17. Ivacaftor did not affect fetal survival at exposures up to 5 times the MRHD (based on summed AUCs of ivacaftor and its metabolites at maternal oral doses up to 200 mg/kg/day). Maternal toxicity was observed at 100 and 200 mg/kg/day (3 and 5 times the exposure at the MRHD) and was associated with a decrease in fetal body weights at a maternal dose of 200 mg/kg/day (5 times the MRHD). In an EFD study, pregnant rabbits were administered ivacaftor at oral doses of 25, 50, or 100 mg/kg/day during the period of organogenesis from gestation Days 7-19. Ivacaftor did not affect fetal development or survival at exposures up to 14 times the MRHD (on an ivacaftor AUC basis at maternal oral doses up to 100 mg/kg/day). Maternal toxicity (i.e., death, decreased food consumption, decreased mean body weight and body weight gain, decreased clinical condition, abortions) was observed at doses greater than or equal to 50 mg/kg/day (approximately 5 times the MRHD). In a PPND study, pregnant rats were administered ivacaftor at oral doses of 50, 100, or 200 mg/kg/day from gestation Day 7 through lactation Day 20. Ivacaftor had no effects on delivery or growth and development of offspring at exposures up to 3 times the MRHD (based on summed AUCs for ivacaftor and its metabolites at maternal oral doses up to 100 mg/kg/day). Decreased fetal body weights were observed at a maternally toxic dose that produced exposures 5 times the MRHD (based on summed AUCs of ivacaftor and its metabolites). Placental transfer of ivacaftor was observed in pregnant rats and rabbits.

8.2 Lactation

Risk Summary

There is no information regarding the presence of elexacaftor, tezacaftor, or ivacaftor in human milk, the effects on the breastfed infant, or the effects on milk production. Elexacaftor, tezacaftor, and ivacaftor are excreted into the milk of lactating rats (see Data). The developmental and health benefits of breastfeeding should be considered along with the mother's clinical need for TRIKAFTA and any potential adverse effects on the breastfed child from TRIKAFTA or from the underlying maternal condition.

Data

Elexacaftor: Lacteal excretion of elexacaftor in rats was demonstrated following a single oral dose (10 mg/kg) of ^14C-elexacaftor administered 6 to 10 days postpartum to lactating dams. Exposure of ^14C-elexacaftor in milk was approximately 0.4 times the value observed in plasma (based on AUC0-72h).

Tezacaftor: Lacteal excretion of tezacaftor in rats was demonstrated following a single oral dose (30 mg/kg) of ^14C-tezacaftor administered 6 to 10 days postpartum to lactating dams. Exposure of ^14C-tezacaftor in milk was approximately 3 times higher than in plasma (based on AUC0-72h).

Ivacaftor: Lacteal excretion of ivacaftor in rats was demonstrated following a single oral dose (100 mg/kg) of ^14C-ivacaftor administered 9 to 10 days postpartum to lactating dams. Exposure of ^14C-ivacaftor in milk was approximately 1.5 times higher than in plasma (based on AUC0-24h).

8.4 Pediatric Use

The safety and effectiveness of TRIKAFTA for the treatment of CF have been established in pediatric patients aged 2 to less than 18 years who have at least one F508del mutation in the CFTR gene or a mutation in the CFTR gene that is responsive based on clinical and/or in vitro data. Use of TRIKAFTA for this indication for pediatric patients 12 years of age and older was supported by evidence from two adequate and well-controlled studies (Trials 1 and 2) in CF patients aged 12 years and older [see Adverse Reactions (6.1) and Clinical Studies (14)].

Use of TRIKAFTA for this indication in pediatric patients 2 to less than 12 years of age is based on the following:

- Trial 1, 56 pediatric patients aged 12 to less than 18 years who had an F508del mutation on one allele and a mutation on the second allele that results in either no CFTR protein or a CFTR protein that is not responsive to ivacaftor and tezacaftor/ivacaftor [see Adverse Reactions (6) and Clinical Studies (14)].
- Trial 2, 16 pediatric patients aged 12 to less than 18 years who were homozygous for the F508del mutation [see Adverse Reactions (6) and Clinical Studies (14)].
- Trial 3, 66 pediatric patients aged 6 to less than 12 years who were homozygous for the F508del mutation or heterozygous for the F508del mutation with a mutation on the second allele that results in either no CFTR protein or a CFTR protein that is not responsive to ivacaftor and tezacaftor/ivacaftor [see Adverse Reactions (6) and Clinical Pharmacology (12.3)].
- Trial 4, 75 pediatric patients aged 2 to less than 6 years who had at least one F508del mutation or a mutation known to be responsive to TRIKAFTA [see Adverse Reactions (6) and Clinical Pharmacology (12.3)].
- Trial 5, 64 pediatric patients aged 6 years to less than 18 years who had a least one qualifying non-F508del TRIKAFTA-responsive mutation and did not have an exclusionary mutation [see Adverse Reactions (6) and Clinical Studies (14.2)].

The effectiveness of TRIKAFTA in patients aged 2 to less than 12 years was extrapolated from patients aged 12 years and older with support from population pharmacokinetic analyses showing elexacaftor, tezacaftor, and ivacaftor exposure levels in patients aged 2 to less than 12 years within the range of exposures observed in patients aged 12 years and older [see Clinical Pharmacology (12.3)]. Safety of TRIKAFTA in patients aged 6 to less than 12 years was derived from a 24-week, open-label, clinical trial in 66 patients aged 6 to less than 12 years (mean age at baseline 9.3 years) administered either a total dose of elexacaftor 100 mg/tezacaftor 50 mg/ivacaftor 75 mg in the morning and ivacaftor 75 mg in the evening (for patients weighing less than 30 kg) or a total dose of elexacaftor 200 mg/tezacaftor 100 mg/ivacaftor 150 mg in the morning and ivacaftor 150 mg in the evening (for patients weighing 30 kg or more) (Trial 3). Safety of TRIKAFTA in patients aged 2 to less than 6 years was derived from a 24-week, open-label, clinical trial in 75 patients aged 2 to less than 6 years (mean age at baseline 4.1 years) administered either a total dose of elexacaftor 80 mg/tezacaftor 40 mg/ivacaftor 60 mg in the morning and ivacaftor 59.5 mg in the evening (for patients weighing 10 kg to less than 14 kg) or a total dose of elexacaftor 100 mg/tezacaftor 50 mg/ivacaftor 75 mg in the morning and ivacaftor 75 mg in the evening (for patients weighing 14 kg or more) (Trial 4). The safety profile of patients in these trials was similar to that observed in Trial 1 [see Adverse Reactions (6)].

The safety and effectiveness of TRIKAFTA in patients with CF younger than 2 years of age have not been established.

Juvenile Animal Toxicity Data

Findings of cataracts were observed in juvenile rats dosed from postnatal Day 7 through 35 with ivacaftor dose levels of 10 mg/kg/day and higher (0.21 times the MRHD based on systemic exposure of ivacaftor and its metabolites). This finding has not been observed in older animals [see Warnings and Precautions (5.6)].

Studies were conducted with tezacaftor in juvenile rats starting at postnatal day (PND) 21 and ranging up to PNDs 35 to 49. Findings of convulsions and death were observed in juvenile rats that received a tezacaftor dose level of 100 mg/kg/day (approximately equivalent to 1.9 times the MRHD based on summed AUCs of tezacaftor and its metabolite, M1-TEZ). A no-effect dose level was identified at 30 mg/kg/day (approximately equivalent to 0.8 times the MRHD based on summed AUCs of tezacaftor and its metabolite, M1-TEZ). Findings were dose related and generally more severe when dosing with tezacaftor was initiated earlier in the postnatal period (PND 7, which would be approximately equivalent to a human neonate). Tezacaftor and its metabolite, M1-TEZ, are substrates for P-glycoprotein. Lower brain levels of P-glycoprotein activity in younger rats resulted in higher brain levels of tezacaftor and M1-TEZ. These findings are not relevant for the indicated pediatric population, 2 years of age and older, for whom levels of P-glycoprotein activity are equivalent to levels observed in adults.

8.5 Geriatric Use

Clinical studies of TRIKAFTA did not include any patients aged 65 years and older.

8.6 Renal Impairment

TRIKAFTA has not been studied in patients with severe renal impairment or end-stage renal disease. No dosage adjustment is recommended in patients with mild (eGFR 60 to <90 mL/min/1.73 m^2) or moderate (eGFR 30 to <60 mL/min/1.73 m^2) renal impairment. Use with caution in patients with severe (eGFR <30 mL/min/1.73 m^2) renal impairment or end-stage renal disease [see Clinical Pharmacology (12.3)].

8.7 Hepatic Impairment

- Severe Hepatic Impairment (Child-Pugh Class C): Should not be used. TRIKAFTA has not been studied in patients with severe hepatic impairment (Child-Pugh Class C), but the exposure is expected to be higher than in patients with moderate hepatic impairment [see Dosage and Administration (2.3), Warnings and Precautions (5.1), Adverse Reactions (6) and Clinical Pharmacology (12.3)].
- Moderate Hepatic Impairment (Child-Pugh Class B): Treatment is not recommended. Use of TRIKAFTA in patients with moderate hepatic impairment should only be considered when there is a clear medical need, and the benefit outweighs the risk. If used in patients with moderate hepatic impairment, TRIKAFTA should be used at a reduced dose. Liver function tests should be closely monitored [see Dosage and Administration (2.1, 2.3) and Warnings and Precautions (5.1)].
  In a clinical study of 11 subjects with moderate hepatic impairment, one subject developed total and direct bilirubin elevations >2 × ULN, and a second subject developed direct bilirubin elevation >4.5 × ULN [see Clinical Pharmacology (12.3)].
- Mild Hepatic Impairment (Child-Pugh Class A): No dose modification is recommended. Liver function tests should be closely monitored [see Dosage and Administration (2.1) and Warnings and Precautions (5.1)].

8.8 Patients with Severe Lung Dysfunction

Trial 1 included a total of 18 patients receiving TRIKAFTA with ppFEV1 <40 at baseline. The safety and efficacy in this subgroup were comparable to those observed in the overall population.

10 OVERDOSAGE

Treatment of overdosage consists of general supportive measures including monitoring of vital signs and observation of the clinical status of the patient.

11 DESCRIPTION

TRIKAFTA is a co-package of elexacaftor, tezacaftor and ivacaftor fixed-dose combination tablets or granules and ivacaftor tablets or granules. Both tablets and granules are for oral administration.

The elexacaftor, tezacaftor and ivacaftor fixed-dose combination tablets are available as: orange, oblong-shaped, film-coated tablet containing 100 mg of elexacaftor, 50 mg of tezacaftor, 75 mg of ivacaftor, or light orange, oblong-shaped, film-coated tablet containing 50 mg of elexacaftor, 25 mg of tezacaftor, 37.5 mg of ivacaftor. The fixed-dose combination tablet contains the following inactive ingredients: croscarmellose sodium, hypromellose, hypromellose acetate succinate, magnesium stearate, microcrystalline cellulose, and sodium lauryl sulfate. The tablet film coat contains hydroxypropyl cellulose, hypromellose, iron oxide red, iron oxide yellow, talc, and titanium dioxide.

The ivacaftor tablet is available as a light blue, oblong-shaped, film-coated tablet containing 150 mg or 75 mg of ivacaftor and the following inactive ingredients: colloidal silicon dioxide, croscarmellose sodium, hypromellose acetate succinate, lactose monohydrate, magnesium stearate, microcrystalline cellulose and sodium lauryl sulfate. The tablet film coat contains carnauba wax, FD&C Blue #2, PEG 3350, polyvinyl alcohol, talc, and titanium dioxide. The printing ink contains ammonium hydroxide, iron oxide black, propylene glycol, and shellac.

The elexacaftor, tezacaftor and ivacaftor fixed-dose combination oral granules are white to off-white, sweetened, unflavored granules approximately 2 mm in diameter enclosed in unit-dose packets. Each unit-dose packet contains 100 mg of elexacaftor, 50 mg of tezacaftor, 75 mg of ivacaftor or 80 mg of elexacaftor, 40 mg of tezacaftor, 60 mg of ivacaftor and the following inactive ingredients: colloidal silicon dioxide, croscarmellose sodium, hypromellose, hypromellose acetate succinate, lactose monohydrate, magnesium stearate, mannitol, sodium lauryl sulfate, and sucralose.

The ivacaftor oral granules are white to off-white, sweetened, unflavored granules approximately 2 mm in diameter enclosed in unit-dose packets. Each unit-dose packet contains 75 mg or 59.5 mg of ivacaftor and the following inactive ingredients: colloidal silicon dioxide, croscarmellose sodium, hypromellose acetate succinate, lactose monohydrate, magnesium stearate, mannitol, sodium lauryl sulfate, and sucralose.

The active ingredients of TRIKAFTA are described below.

Elexacaftor

Elexacaftor is a white solid that is practically insoluble in water (<1 mg/mL). Its chemical name is N-(1,3-dimethyl-1H-pyrazole-4-sulfonyl)-6-[3-(3,3,3-trifluoro-2,2-dimethylpropoxy)-1H-pyrazol-1-yl]-2-[(4S)-2,2,4-trimethylpyrrolidin-1-yl]pyridine-3-carboxamide. Its molecular formula is C26H34N7O4SF3 and its molecular weight is 597.66. Elexacaftor has the following structural formula:

Tezacaftor

Tezacaftor is a white to off-white solid that is practically insoluble in water (<5 microgram/mL). Its chemical name is 1-(2,2-difluoro-2H-1,3-benzodioxol-5-yl)-N-{1-[(2R)-2,3-dihydroxypropyl]-6-fluoro-2-(1-hydroxy-2-methylpropan-2-yl)-1H-indol-5-yl}cyclopropane-1-carboxamide. Its molecular formula is C26H27N2F3O6 and its molecular weight is 520.50. Tezacaftor has the following structural formula:

Ivacaftor

Ivacaftor is a white to off-white crystalline solid that is practically insoluble in water (<0.05 microgram/mL). Pharmacologically it is a CFTR potentiator. Its chemical name is N-(2,4-di-tert-butyl-5-hydroxyphenyl)-1,4-dihydro-4-oxoquinoline-3-carboxamide. Its molecular formula is C24H28N2O3 and its molecular weight is 392.49. Ivacaftor has the following structural formula:

12 CLINICAL PHARMACOLOGY

12.1 Mechanism of Action

Elexacaftor and tezacaftor bind to different sites on the CFTR protein and have an additive effect in facilitating the cellular processing and trafficking of select mutant forms of CFTR (including F508del-CFTR) to increase the amount of CFTR protein delivered to the cell surface compared to either molecule alone. Ivacaftor potentiates the channel open probability (or gating) of the CFTR protein at the cell surface.

The combined effect of elexacaftor, tezacaftor and ivacaftor is increased quantity and function of CFTR at the cell surface, resulting in increased CFTR activity as measured both by CFTR mediated chloride transport in vitro and by sweat chloride in patients with CF.

CFTR Chloride Transport Assay in Fischer Rat Thyroid Cells Expressing Mutant CFTR Protein

Effects of elexacaftor/tezacaftor/ivacaftor on chloride transport for mutant CFTR proteins was determined in Ussing chamber electrophysiology studies using a panel of Fischer Rat Thyroid (FRT) cell lines stably expressing individual mutant CFTR protein. Elexacaftor/tezacaftor/ivacaftor increased chloride transport in FRT cells expressing CFTR mutations, as identified in Table 6.

The threshold that the treatment-induced increase in chloride transport must exceed for the mutant CFTR protein to be considered responsive is ≥10% of normal over baseline. This threshold was used because it is expected to predict clinical benefit. For individual mutations, the magnitude of the net change over baseline in CFTR-mediated chloride transport in vitro is not correlated with the magnitude of clinical response.

CFTR Chloride Transport Assay in Human Bronchial Epithelial Cells Expressing Mutant CFTR Protein

Homozygous and heterozygous N1303K-Human Bronchial Epithelial (HBE) cells showed greater chloride transport in the presence of elexacaftor/tezacaftor/ivacaftor than F508del/F508del-HBE cells treated with tezacaftor/ivacaftor (which has shown clinical benefit in people homozygous for F508del).

Patient Selection

Select patients 2 years of age and older for treatment of CF with TRIKAFTA based on the presence of at least one F508del mutation or another responsive mutation in the CFTR gene (see Table 6) [see Indications and Usage (1)].

Table 6 lists CFTR mutations responsive to TRIKAFTA based on clinical response and/or in vitro data in FRT or HBE cells or based on extrapolation of efficacy.

Table 6: List of CFTR Gene Mutations Responsive to TRIKAFTA
Mutations responsive to TRIKAFTA based on clinical data [Clinical data obtained from Trials 1, 2, and 5.]
2789+5G→A | D1152H [This mutation is also predicted to be responsive by FRT assay.] | L206W | R1066H | S945L
3272-26A→G | F508del | L997F | R117C | T338I
3849+10kbC→T | G85E | M1101K | R347H | V232D
A455E | L1077P | P5L | R347P
Mutations responsive to TRIKAFTA based on in vitro data [The N1303K mutation is predicted to be responsive by HBE assay. All other mutations predicted to be responsive with in vitro data are supported by FRT assay.]
N1303K | F200I | I1139V | P574H | S1045Y
1507_1515del9 | F311del | I125T | P67L | S108F
2183A→G | F311L | I1269N | P750L | S1118F
3141del9 | F508C | I1366N | Q1291R | S1159F
546insCTA | F508C;S1251N | I148N | Q1313K | S1159P
A1006E | F575Y | I148T | Q237E | S1235R
A1067P | F587I | I175V | Q237H | S1251N
A1067T | G1047R | I331N | Q359R | S1255P
A107G | G1061R | I336K | Q372H | S13F
A120T | G1069R | I502T | Q493R | S341P
A234D | G1123R | I506L | Q552P | S364P
A309D | G1244E | I556V | Q98R | S492F
A349V | G1247R | I601F | R1048G | S549I
A46D | G1249R | I618T | R1070Q | S549N
A554E | G126D | I807M | R1070W | S549R
A62P | G1349D | I980K | R1162L | S589N
C491R | G178E | K1060T | R117C;G576A;R668C | S737F
D110E | G178R | K162E | R117G | S912L
D110H | G194R | K464E | R117H | S977F
D1270N | G194V | L1011S | R117L | T1036N
D1445N | G27E | L1324P | R117P | T1053I
D192G | G27R | L1335P | R1283M | T1086I
D443Y | G314E | L137P | R1283S | T1246I
D443Y;G576A;R668C | G424S | L1480P | R170H | T1299I
D565G | G463V | L15P | R258G | T351I
D579G | G480C | L165S | R297Q | V1153E
D614G | G480S | L320V | R31C | V1240G
D836Y | G551A | L333F | R31L | V1293G
D924N | G551D | L333H | R334L | V201M
D979V | G551S | L346P | R334Q | V392G
D993Y | G576A | L441P | R347L | V456A
E116K | G576A;R668C | L453S | R352Q | V456F
E116Q | G622D | L619S | R352W | V562I
E193K | G628R | L967S | R516S | V603F
E292K | G970D | M1137V | R553Q | V754M
E403D | G970S | M150K | R555G | W1098C
E474K | H1054D | M152V | R668C | W1282R
E56K | H1085P | M265R | R709Q | W361R
E588V | H1085R | M952I | R74Q | Y1014C
E60K | H1375P | M952T | R74W | Y1032C
E822K | H139R | N1088D | R74W;D1270N | Y109N
E92K | H199Y | N1303I | R74W;V201M | Y161D
F1016S | H620P | N186K | R74W;V201M;D1270N | Y161S
F1052V | H620Q | N187K | R751L | Y301C
F1074L | H939R | N418S | R75L | Y563N
F1099L | H939R;H949L | P140S | R75Q
F1107L | I1027T | P205S | R792G
F191V | I105N | P499A | R933G
Mutations responsive to TRIKAFTA based on extrapolation from Trial 5 [Efficacy is extrapolated from Trial 5 to non-canonical splice mutations because clinical trials in all mutations of this subgroup are infeasible and these mutations are not amenable to interrogation by FRT system.]
4005+2T→C | 2789+2insA | 3849+40A→G | 5T;TG13
1341G→A | 296+28A→G | 3849+4A→G | 621+3A→G
1898+3A→G | 3041-15T→G | 3850-3T→G | 711+3A→G
2752-26A→G | 3600G→A | 5T;TG12 | E831X

12.2 Pharmacodynamics

Sweat Chloride Evaluation

In Trial 1 (patients with an F508del mutation on one allele and a mutation on the second allele that results in either no CFTR protein or a CFTR protein that is not responsive ivacaftor and tezacaftor/ivacaftor), a reduction in sweat chloride was observed from baseline at Week 4 and sustained through the 24-week treatment period [see Clinical Studies (14.1)]. In Trial 2 (patients homozygous for the F508del mutation), a reduction in sweat chloride was observed from baseline at Week 4 [see Clinical Studies (14.2)]. In Trial 3 (patients aged 6 to less than 12 years who are homozygous for the F508del mutation or heterozygous for the F508del mutation and a mutation on the second allele that results in either no CFTR protein or a CFTR protein that is not responsive to ivacaftor and tezacaftor/ivacaftor), the mean absolute change in sweat chloride from baseline through Week 24 was -60.9 mmol/L (95% CI: -63.7, -58.2). In Trial 4 (patients aged 2 to less than 6 years who had at least one F508del mutation or a mutation known to be responsive to TRIKAFTA), the mean absolute change in sweat chloride from baseline through Week 24 was -57.9 mmol/L (95% CI: -61.3, -54.6). In Trial 5 (patients aged 6 years and older with at least one qualifying non-F508del elexacaftor/tezacaftor/ivacaftor-responsive CFTR mutation), the mean absolute change in sweat chloride from baseline through Week 24 compared to placebo was -28.3 mmol/L (95% CI: -32.1, -24.5).

Cardiac Electrophysiology

At doses up to 2 times the maximum recommended dose of elexacaftor and 3 times the maximum recommended dose of tezacaftor and ivacaftor, the QT/QTc interval in healthy subjects was not prolonged to any clinically relevant extent.

12.3 Pharmacokinetics

The pharmacokinetics of elexacaftor, tezacaftor and ivacaftor are similar between healthy adult subjects and patients with CF. The pharmacokinetic parameters for elexacaftor, tezacaftor and ivacaftor in patients with CF aged 12 years and older are shown in Table 7.

Table 7: Pharmacokinetic Parameters of TRIKAFTA Components
 | Elexacaftor | Tezacaftor | Ivacaftor
General Information
AUCss (SD), mcg∙h/mL [Based on elexacaftor 200 mg and tezacaftor 100 mg once daily/ivacaftor 150 mg every 12 hours at steady state in patients with CF aged 12 years and older.] | 162 (47.5) [AUC0-24h.] | 89.3 (23.2) | 11.7 (4.01) [AUC0-12h.]
Cmax (SD), mcg/mL | 9.2 (2.1) | 7.7 (1.7) | 1.2 (0.3)
Time to Steady State, days | Within 7 days | Within 8 days | Within 3-5 days
Accumulation Ratio | 2.2 | 2.07 | 2.4
Absorption
Absolute Bioavailability | 80% | Not determined | Not determined
Median Tmax (range), hours | 6 (4 to 12) | 3 (2 to 4) | 4 (3 to 6)
Effect of Food | AUC increases 1.9- to 2.5-fold (moderate-fat meal) | No clinically significant effect | Exposure increases 2.5- to 4-fold
Distribution
Mean (SD) Apparent Volume of Distribution, L [Elexacaftor, tezacaftor and ivacaftor do not partition preferentially into human red blood cells.] | 53.7 (17.7) | 82.0 (22.3) | 293 (89.8)
Protein Binding [Elexacaftor and tezacaftor bind primarily to albumin. Ivacaftor primarily bind to albumin, alpha 1-acid glycoprotein and human gamma-globulin.] | >99% | approximately 99% | approximately 99%
Elimination
Mean (SD) Effective Half-Life, hours [Mean (SD) terminal half-lives of elexacaftor, tezacaftor and ivacaftor are approximately 24.7 (4.87) hours, 60.3 (15.7) hours and 13.1 (2.98) hours, respectively.] | 27.4 (9.31) | 25.1 (4.93) | 15.0 (3.92)
Mean (SD) Apparent Clearance, L/hours | 1.18 (0.29) | 0.79 (0.10) | 10.2 (3.13)
Metabolism
Primary Pathway | CYP3A4/5 | CYP3A4/5 | CYP3A4/5
Active Metabolites | M23-ELX | M1-TEZ | M1-IVA
Metabolite Potency Relative to Parent | Similar | Similar | approximately 1/6th of parent
Excretion [Following radiolabeled doses.]
Primary Pathway | - Feces: 87.3% (primarily as metabolites) - Urine: 0.23% | - Feces: 72% (unchanged or as M2-TEZ) - Urine: 14% (0.79% unchanged) | - Feces: 87.8% - Urine: 6.6%
AUCss: area under the concentration versus time curve at steady state; SD: Standard Deviation; Cmax: maximum observed concentration; Tmax: time of maximum concentration; AUC: area under the concentration versus time curve.

Specific Populations

Pediatric Patients 2 to Less Than 12 Years of Age

Elexacaftor, tezacaftor and ivacaftor exposures observed in patients aged 2 to less than 12 years as determined using population PK analysis are presented by age group and dose administered in Table 8. Elexacaftor, tezacaftor and ivacaftor exposures in this patient population are within the range observed in patients aged 12 years and older.

Table 8: Mean (SD) Elexacaftor, Tezacaftor and Ivacaftor Exposures Observed at Steady State by Age Group and Dose Administered
Age Group | Dose | Elexacaftor AUC0-24h,ss (µg∙h/mL) | Tezacaftor AUC0-24h,ss (µg∙h/mL) | Ivacaftor AUC0-12h,ss (µg∙h/mL)
Patients aged 2 to less than 6 years weighing less than 14 kg (N = 16) | elexacaftor 80 mg qd/tezacaftor 40 mg qd/ivacaftor 60 mg qAM and ivacaftor 59.5 mg qPM | 128 (24.8) | 87.3 (17.3) | 11.9 (3.86)
Patients aged 2 to less than 6 years weighing 14 kg or more (N = 59) | elexacaftor 100 mg qd/tezacaftor 50 mg qd/ivacaftor 75 mg q12h | 138 (47.0) | 90.2 (27.9) | 13.0 (6.11)
Patients aged 6 to less than 12 years weighing less than 30 kg (N = 36) | elexacaftor 100 mg qd/tezacaftor 50 mg qd/ivacaftor 75 mg q12h | 116 (39.4) | 67.0 (22.3) | 9.78 (4.50)
Patients aged 6 to less than 12 years weighing 30 kg or more (N = 30) | elexacaftor 200 mg qd/ tezacaftor 100 mg qd/ ivacaftor 150 mg q12h | 195 (59.4) | 103 (23.7) | 17.5 (4.97)
SD: Standard Deviation; AUCss: area under the concentration versus time curve at steady state.

Pediatric Patients 12 to Less Than 18 Years of Age

The following conclusions about exposures between adults and the pediatric population are based on population pharmacokinetic (PK) analyses. Following oral administration of TRIKAFTA to patients 12 to less than 18 years of age (elexacaftor 200 mg qd/tezacaftor 100 mg qd/ivacaftor 150 mg q12h), the mean (±SD) AUCss was 147 (36.8) mcg∙h/mL, 88.8 (21.8) mcg∙h/mL and 10.6 (3.35) mcg∙h/mL, respectively for elexacaftor, tezacaftor and ivacaftor, similar to the AUCss in adult patients.

Patients with Renal Impairment

Renal excretion of elexacaftor, tezacaftor and ivacaftor is minimal. Elexacaftor alone or in combination with tezacaftor and ivacaftor has not been studied in subjects with severe (eGFR <30 mL/min/1.73 m^2) renal impairment or end-stage renal disease. Based on population PK analyses, the clearance of elexacaftor and tezacaftor was similar in subjects with mild (eGFR 60 to <90 mL/min/1.73 m^2) or moderate (eGFR 30 to <60 mL/min/1.73 m^2) renal impairment relative to patients with normal renal function [see Use in Specific Populations (8.6)].

Patients with Hepatic Impairment

Elexacaftor alone or in combination with tezacaftor and ivacaftor has not been studied in subjects with severe hepatic impairment (Child-Pugh Class C, score 10-15). In a clinical study, following multiple doses of elexacaftor, tezacaftor and ivacaftor for 10 days, subjects with moderately impaired hepatic function (Child-Pugh Class B, score 7-9) had 25% higher AUC and 12% higher Cmax for elexacaftor, 73% higher AUC and 70% higher Cmax for M23-ELX, 36% higher AUC and 24% higher Cmax for combined elexacaftor and M23-ELX, 20% higher AUC but similar Cmax for tezacaftor and 1.5-fold higher AUC and 10% higher Cmax for ivacaftor compared with healthy subjects matched for demographics [see Dosage and Administration (2.3), Warnings and Precautions (5.1), Adverse Reactions (6) and Use in Specific Populations (8.7)].

Tezacaftor and Ivacaftor

Following multiple doses of tezacaftor and ivacaftor for 10 days, subjects with moderately impaired hepatic function had an approximately 36% higher AUC and a 10% higher in Cmax for tezacaftor and a 1.5-fold higher AUC but similar Cmax for ivacaftor compared with healthy subjects matched for demographics.

Ivacaftor

In a study with ivacaftor alone, subjects with moderately impaired hepatic function had similar ivacaftor Cmax, but an approximately 2.0-fold higher ivacaftor AUC0-∞ compared with healthy subjects matched for demographics.

Male and Female Patients

Based on population PK analysis, the exposures of elexacaftor, tezacaftor and ivacaftor are similar in males and females.

Drug Interaction Studies

Drug interaction studies were performed with elexacaftor, tezacaftor and/or ivacaftor and other drugs likely to be co-administered or drugs commonly used as probes for pharmacokinetic interaction studies [see Drug Interactions (7)].

Potential for Elexacaftor, Tezacaftor and/or Ivacaftor to Affect Other Drugs

Based on in vitro results, elexacaftor and tezacaftor have a low potential to inhibit CYP1A2, CYP2B6, CYP2C8, CYP2C9, CYP2C19, CYP2D6 and CYP3A4, whereas ivacaftor has the potential to inhibit CYP2C8, CYP2C9 and CYP3A. However, clinical studies showed that the combination regimen of tezacaftor/ivacaftor is not an inhibitor of CYP3A and ivacaftor is not an inhibitor of CYP2C8 or CYP2D6.

Based on in vitro results, elexacaftor, tezacaftor and ivacaftor are not likely to induce CYP3A, CYP1A2 and CYP2B6.

Based on in vitro results, elexacaftor and tezacaftor have a low potential to inhibit the transporter P-gp, while ivacaftor has the potential to inhibit P-gp. Co-administration of tezacaftor/ivacaftor with digoxin, a sensitive P-gp substrate, increased digoxin exposure by 1.3-fold in a clinical study. Based on in vitro results, elexacaftor and M23-ELX may inhibit OATP1B1 and OATP1B3 uptake. Tezacaftor has a low potential to inhibit BCRP, OCT2, OAT1, or OAT3. Ivacaftor is not an inhibitor of the transporters OCT1, OCT2, OAT1, or OAT3.

The effects of elexacaftor, tezacaftor and/or ivacaftor on the exposure of co-administered drugs are shown in Table 9 [see Drug Interactions (7)].

Table 9: Impact of Elexacaftor, Tezacaftor and/or Ivacaftor on Other Drugs
Dose and Schedule |  | Effect on Other Drug PK | Geometric Mean Ratio (90% CI) of Other Drug No Effect=1.0
 |  | Effect on Other Drug PK | AUC | Cmax
Midazolam 2 mg single oral dose | TEZ 100 mg qd/IVA 150 mg q12h | ↔ Midazolam | 1.12 (1.01, 1.25) | 1.13 (1.01, 1.25)
Digoxin 0.5 mg single dose | TEZ 100 mg qd/IVA 150 mg q12h | ↑ Digoxin | 1.30 (1.17, 1.45) | 1.32 (1.07, 1.64)
Oral Contraceptive Ethinyl estradiol 30 µg/Levonorgestrel 150 µg qd | ELX 200 mg qd/TEZ 100 mg qd/IVA 150 mg q12h | ↑ Ethinyl estradiol [Effect is not clinically significant [see Drug Interactions (7.3)].] | 1.33 (1.20, 1.49) | 1.26 (1.14, 1.39)
Oral Contraceptive Ethinyl estradiol 30 µg/Levonorgestrel 150 µg qd | ELX 200 mg qd/TEZ 100 mg qd/IVA 150 mg q12h | ↑ Levonorgestrel | 1.23 (1.10, 1.37) | 1.10 (0.985, 1.23)
Rosiglitazone 4 mg single oral dose | IVA 150 mg q12h | ↔ Rosiglitazone | 0.975 (0.897, 1.06) | 0.928 (0.858, 1.00)
Desipramine 50 mg single dose | IVA 150 mg q12h | ↔ Desipramine | 1.04 (0.985, 1.10) | 1.00 (0.939, 1.07)
↑ = increase, ↓ = decrease, ↔ = no change.
AUC: area under the concentration versus time curve; CI: Confidence Interval; ELX: elexacaftor; Cmax: maximum observed concentration; TEZ: tezacaftor; IVA: ivacaftor; PK: Pharmacokinetics.

Potential for Other Drugs to Affect Elexacaftor, Tezacaftor and/or Ivacaftor

In vitro studies showed that elexacaftor, tezacaftor and ivacaftor are all metabolized by CYP3A. Exposure to elexacaftor, tezacaftor and ivacaftor may be reduced by concomitant CYP3A inducers and increased by concomitant CYP3A inhibitors.

In vitro studies showed that elexacaftor and tezacaftor are substrates for the efflux transporter P-gp, but ivacaftor is not. Elexacaftor and ivacaftor are not substrates for OATP1B1 or OATP1B3; tezacaftor is a substrate for OATP1B1, but not OATP1B3. Tezacaftor is a substrate for BCRP.

The effects of co-administered drugs on the exposure of elexacaftor, tezacaftor and/or ivacaftor are shown in Table 10 [see Dosage and Administration (2.4) and Drug Interactions (7)].

Table 10: Impact of Other Drugs on Elexacaftor, Tezacaftor and/or Ivacaftor
Dose and Schedule |  | Effect on ELX, TEZ and/or IVA PK | Geometric Mean Ratio (90% CI) of Elexacaftor, Tezacaftor and Ivacaftor No Effect = 1.0
Dose and Schedule |  | Effect on ELX, TEZ and/or IVA PK | AUC | Cmax
Itraconazole 200 mg q12h on Day 1, followed by 200 mg qd | TEZ 25 mg qd + IVA 50 mg qd | ↑ Tezacaftor | 4.02 (3.71, 4.63) | 2.83 (2.62, 3.07)
Itraconazole 200 mg q12h on Day 1, followed by 200 mg qd | TEZ 25 mg qd + IVA 50 mg qd | ↑ Ivacaftor | 15.6 (13.4, 18.1) | 8.60 (7.41, 9.98)
Itraconazole 200 mg qd | ELX 20 mg + TEZ 50 mg single dose | ↑ Elexacaftor | 2.83 (2.59, 3.10) | 1.05 (0.977, 1.13)
Itraconazole 200 mg qd | ELX 20 mg + TEZ 50 mg single dose | ↑ Tezacaftor | 4.51 (3.85, 5.29) | 1.48 (1.33, 1.65)
Ketoconazole 400 mg qd | IVA 150 mg single dose | ↑ Ivacaftor | 8.45 (7.14, 10.0) | 2.65 (2.21, 3.18)
Ciprofloxacin 750 mg q12h | TEZ 50 mg q12h + IVA 150 mg q12h | ↔ Tezacaftor | 1.08 (1.03, 1.13) | 1.05 (0.99, 1.11)
Ciprofloxacin 750 mg q12h | TEZ 50 mg q12h + IVA 150 mg q12h | ↑ Ivacaftor [Effect is not clinically significant [see Drug Interactions (7.3)].] | 1.17 (1.06, 1.30) | 1.18 (1.06, 1.31)
Rifampin 600 mg qd | IVA 150 mg single dose | ↓ Ivacaftor | 0.114 (0.097, 0.136) | 0.200 (0.168, 0.239)
Fluconazole 400 mg single dose on Day 1, followed by 200 mg qd | IVA 150 mg q12h | ↑ Ivacaftor | 2.95 (2.27, 3.82) | 2.47 (1.93, 3.17)
↑ = increase, ↓ = decrease, ↔ = no change.
AUC: area under the concentration versus time curve; CI: Confidence Interval; Cmax: maximum observed concentration; ELX: elexacaftor; TEZ: tezacaftor; IVA: ivacaftor; PK: Pharmacokinetics.

13 NONCLINICAL TOXICOLOGY

13.1 Carcinogenesis, Mutagenesis, Impairment of Fertility

No studies of carcinogenicity, mutagenicity, or impairment of fertility were conducted with the combination of elexacaftor, tezacaftor and ivacaftor; however, separate studies of elexacaftor, tezacaftor and ivacaftor are described below.

Elexacaftor

A 6-month study in Tg.rasH2 transgenic mice showed no evidence of tumorigenicity at 50 mg/kg/day dose, the highest dose tested.

A two-year study was conducted in rats to assess the carcinogenic potential of elexacaftor. No evidence of tumorigenicity was observed in rats at elexacaftor oral doses up to 10 mg/kg/day (approximately 2 and 5 times the MRHD based on summed AUCs of elexacaftor and its metabolite in male and female rats, respectively).

Elexacaftor was negative for genotoxicity in the following assays: Ames test for bacterial gene mutation, in vitro mammalian cell micronucleus assay in TK6 cells, and in vivo mouse micronucleus test.

Elexacaftor did not cause reproductive system toxicity in male rats at 55 mg/kg/day and female rats at 25 mg/kg/day, equivalent to approximately 6 times and 4 times the MRHD, respectively (based on summed AUCs of elexacaftor and its metabolite). Elexacaftor did not cause embryonic toxicity at 35 mg/kg/day which was the highest dose tested, equivalent to approximately 7 times the MRHD (based on summed AUCs of elexacaftor and its metabolite). Lower male and female fertility, male copulation and female conception indices were observed in males at 75 mg/kg/day and females at 35 mg/kg/day, equivalent to approximately 6 times and 7 times, respectively, the MRHD (based on summed AUCs of elexacaftor and its metabolite).

Tezacaftor

A two-year study in Sprague-Dawley rats and a 6-month study in Tg.rasH2 transgenic mice were conducted to assess the carcinogenic potential of tezacaftor. No evidence of tumorigenicity from tezacaftor was observed in male and female rats at oral doses up to 50 and 75 mg/kg/day (approximately 1 and 2 times the MRHD based on summed AUCs of tezacaftor and its metabolites in males and females, respectively). No evidence of tumorigenicity was observed in male and female Tg.rasH2 transgenic mice at tezacaftor doses up to 500 mg/kg/day.

Tezacaftor was negative for genotoxicity in the following assays: Ames test for bacterial gene mutation, in vitro chromosomal aberration assay in Chinese hamster ovary cells and in vivo mouse micronucleus test.

There were no effects on male or female fertility and early embryonic development in rats at oral tezacaftor doses up to 100 mg/kg/day (approximately 3 times the MRHD based on summed AUC of tezacaftor and M1-TEZ).

Ivacaftor

Two-year studies were conducted in CD-1 mice and Sprague-Dawley rats to assess the carcinogenic potential of ivacaftor. No evidence of tumorigenicity from ivacaftor was observed in mice or rats at oral doses up to 200 mg/kg/day and 50 mg/kg/day, respectively (approximately equivalent to 2 and 7 times the MRHD, respectively, based on summed AUCs of ivacaftor and its metabolites).

Ivacaftor was negative for genotoxicity in the following assays: Ames test for bacterial gene mutation, in vitro chromosomal aberration assay in Chinese hamster ovary cells and in vivo mouse micronucleus test.

Ivacaftor impaired fertility and reproductive performance indices in male and female rats at 200 mg/kg/day (approximately 7 and 5 times, respectively, the MRHD based on summed AUCs of ivacaftor and its metabolites). Increases in prolonged diestrus were observed in females at 200 mg/kg/day. Ivacaftor also increased the number of females with all nonviable embryos and decreased corpora lutea, implantations and viable embryos in rats at 200 mg/kg/day (approximately 5 times the MRHD based on summed AUCs of ivacaftor and its metabolites) when dams were dosed prior to and during early pregnancy. These impairments of fertility and reproductive performance in male and female rats at 200 mg/kg/day were attributed to severe toxicity.

14 CLINICAL STUDIES

14.1 Clinical Studies in Patients with Cystic Fibrosis with at Least One F508del Mutation

The efficacy of TRIKAFTA in patients aged 12 years and older with cystic fibrosis (CF) with at least one F508del mutation was evaluated in two randomized, double-blind, controlled trials (Trials 1 and 2).

Trial 1 (NCT03525444) was a 24-week, randomized, double-blind, placebo-controlled study in patients who had an F508del mutation on one allele and a mutation on the second allele that results in either no CFTR protein or a CFTR protein that is not responsive to ivacaftor and tezacaftor/ivacaftor. An interim analysis was planned when at least 140 patients completed Week 4 and at least 100 patients completed Week 12.

Trial 2 (NCT03525548) was a 4-week, randomized, double-blind, active-controlled study in patients who are homozygous for the F508del mutation. Patients received tezacaftor 100 mg qd/ivacaftor 150 mg q12h during a 4-week, open-label run-in period and were then randomized and dosed to receive TRIKAFTA or tezacaftor 100 mg qd/ivacaftor 150 mg q12h during a 4-week, double-blind treatment period.

Patients in Trials 1 and 2 had a confirmed diagnosis of CF and at least one F508del mutation. Patients discontinued any previous CFTR modulator therapies, but continued on their other standard-of-care CF therapies (e.g., bronchodilators, inhaled antibiotics, dornase alfa and hypertonic saline). Patients had a ppFEV1 at screening between 40-90%. Patients with a history of colonization with organisms associated with a more rapid decline in pulmonary status, including but not limited to Burkholderia cenocepacia, Burkholderia dolosa, or Mycobacterium abscessus, or who had an abnormal liver function test at screening (ALT, AST, ALP, or GGT ≥3 × ULN, or total bilirubin ≥2 × ULN), were excluded from the trials. Patients in Trials 1 and 2 were eligible to roll over into an open-label extension study.

Trial 1

Trial 1 evaluated 403 patients (200 TRIKAFTA, 203 placebo) with CF aged 12 years and older (mean age 26.2 years). The mean ppFEV1 at baseline was 61.4% (range: 32.3%, 97.1%). The primary endpoint assessed at the time of interim analysis was mean absolute change in ppFEV1 from baseline at Week 4. The final analysis tested all key secondary endpoints in the 403 patients who completed the 24-week study participation, including absolute change in ppFEV1 from baseline through Week 24; absolute change in sweat chloride from baseline at Week 4 and through Week 24; number of pulmonary exacerbations through Week 24; absolute change in BMI from baseline at Week 24, and absolute change in CFQ-R respiratory domain score (a measure of respiratory symptoms relevant to patients with CF, such as cough, sputum production and difficulty breathing) from baseline at Week 4 and through Week 24.

Of the 403 patients included in the interim analysis, the treatment difference between TRIKAFTA and placebo for the mean absolute change from baseline in ppFEV1 at Week 4 was 13.8 percentage points (95% CI: 12.1, 15.4; P<0.0001).

The treatment difference between TRIKAFTA and placebo for mean absolute change in ppFEV1 from baseline through Week 24 was 14.3 percentage points (95% CI: 12.7, 15.8; P<0.0001). Mean improvement in ppFEV1 was observed at the first assessment on Day 15 and sustained through the 24-week treatment period (see Figure 1). Improvements in ppFEV1 were observed regardless of age, baseline ppFEV1, sex and geographic region. See Table 11 for a summary of primary and key secondary outcomes in Trial 1.

Table 11: Primary and Key Secondary Efficacy Analyses (Trial 1)
Analysis | Statistic | Treatment Difference [Treatment difference provided as the outcome measure for changes in ppFEV1, sweat chloride, CFQ-R and BMI; Rate ratio provided as the outcome measure for the number of pulmonary exacerbations.] for TRIKAFTA (N=200) vs Placebo (N=203)
Primary (Interim Full Analysis Set) [Primary endpoint was based on interim analysis in 403 patients.]
Absolute change in ppFEV1 from baseline at Week 4 (percentage points) | Treatment difference (95% CI) P value | 13.8 (12.1, 15.4) P<0.0001
Key Secondary (Full Analysis Set) [Key secondary endpoints were tested at the final analysis in 403 patients.]
Absolute change in ppFEV1 from baseline through Week 24 (percentage points) | Treatment difference (95% CI) P value | 14.3 (12.7, 15.8) P<0.0001
Number of pulmonary exacerbations from baseline through Week 24 [A pulmonary exacerbation was defined as a change in antibiotic therapy (IV, inhaled, or oral) as a result of 4 or more of 12 pre-specified sino-pulmonary signs/symptoms.] [Number of pulmonary exacerbation events (event rate per year calculated based on 48 weeks per year) in the TRIKAFTA group were 41 (0.37) and 113 (0.98) in the placebo group.] | Rate ratio (95% CI) P value | 0.37 (0.25, 0.55) P<0.0001
Absolute change in sweat chloride from baseline through Week 24 (mmol/L) | Treatment difference (95% CI) P value | -41.8 (-44.4, -39.3) P<0.0001
Absolute change in CFQ-R respiratory domain score from baseline through Week 24 (points) | Treatment difference (95% CI) P value | 20.2 (17.5, 23.0) P<0.0001
Absolute change in BMI from baseline at Week 24 (kg/m^2) | Treatment difference (95% CI) P value | 1.04 (0.85, 1.23) P<0.0001
Absolute change in sweat chloride from baseline at Week 4 (mmol/L) | Treatment difference (95% CI) P value | -41.2 (-44.0, -38.5) P<0.0001
Absolute change in CFQ-R respiratory domain score from baseline at Week 4 (points) | Treatment difference (95% CI) P value | 20.1 (16.9, 23.2) P<0.0001
ppFEV1: percent predicted Forced Expiratory Volume in 1 second; CI: Confidence Interval; CFQ-R: Cystic Fibrosis Questionnaire-Revised; BMI: Body Mass Index.

Figure 1: Absolute Change from Baseline in Percent Predicted FEV1 at Each Visit in Trial 1

Trial 2

Trial 2 evaluated 107 patients with CF aged 12 years and older (mean age 28.4 years). The mean ppFEV1 at baseline, following the 4-week, open-label run-in period with tezacaftor/ivacaftor was 60.9% (range: 35.0%, 89.0%). The primary endpoint was mean absolute change in ppFEV1 from baseline at Week 4 of the double-blind treatment period. The key secondary efficacy endpoints were absolute change in sweat chloride and CFQ-R respiratory domain score from baseline at Week 4. Treatment with TRIKAFTA compared to tezacaftor/ivacaftor resulted in a statistically significant improvement in ppFEV1 of 10.0 percentage points (95% CI: 7.4, 12.6; P<0.0001). Mean improvement in ppFEV1 was observed at the first assessment on Day 15. Improvements in ppFEV1 were observed regardless of age, sex, baseline ppFEV1 and geographic region. See Table 12 for a summary of primary and key secondary outcomes.

Table 12: Primary and Key Secondary Efficacy Analyses, Full Analysis Set (Trial 2)
Analysis [Baseline for primary and key secondary endpoints is defined as the end of the 4-week tezacaftor/ivacaftor run-in period.] | Statistic | Treatment Difference for TRIKAFTA (N=55) vs Tezacaftor/Ivacaftor [Regimen of tezacaftor 100 mg qd/ivacaftor 150 mg q12h.] (N=52)
Primary
Absolute change in ppFEV1 from baseline at Week 4 (percentage points) | Treatment difference (95% CI) P value | 10.0 (7.4, 12.6) P<0.0001
Key Secondary
Absolute change in sweat chloride from baseline at Week 4 (mmol/L) | Treatment difference (95% CI) P value | -45.1 (-50.1, -40.1) P<0.0001
Absolute change in CFQ-R respiratory domain score from baseline at Week 4 (points) | Treatment difference (95% CI) P value | 17.4 (11.8, 23.0) P<0.0001
ppFEV1: percent predicted Forced Expiratory Volume in 1 second; CI: Confidence Interval; CFQ-R: Cystic Fibrosis Questionnaire-Revised.

14.2 Clinical Studies in Patients with Cystic Fibrosis with at Least One Qualifying Non-F508del Mutation

The efficacy of TRIKAFTA in patients with cystic fibrosis (CF) without an F508del mutation was evaluated in Trial 5.

Trial 5 (NCT05274269) was a 24-week, randomized, placebo-controlled, double-blind, parallel-group trial in 307 patients aged 6 years and older with CF (mean age 33.5 years). The mean baseline ppFEV1 was 67.7% (range: 34.0%, 108.7%). The trial included patients who had at least one qualifying non-F508del TRIKAFTA-responsive mutation and did not have an exclusionary mutation. Patients were randomized to TRIKAFTA or placebo. The dosage of TRIKAFTA was administered according to age and weight as follows:

- Patients aged 6 to less than 12 years, weighing less than 30 kg: total morning dose of elexacaftor 100 mg/ tezacaftor 50 mg/ ivacaftor 75 mg and evening dose of ivacaftor 75 mg
- Patients aged 6 to less than 12 years, weighing greater than or equal to 30 kg: total morning dose of elexacaftor 200 mg/ tezacaftor 100 mg/ ivacaftor 150 mg and evening dose of ivacaftor 150 mg
- Patients aged 12 years and older: total morning dose of elexacaftor 200 mg/ tezacaftor 100 mg/ ivacaftor 150 mg and evening dose of ivacaftor 150 mg

Patients discontinued any previous CFTR modulator therapies but continued on their other standard-of-care CF therapies (e.g., bronchodilators, inhaled antibiotics, dornase alfa and hypertonic saline). Patients had a ppFEV1 between 40-100% at screening. The mean ppFEV1 at baseline was 68% (range: 34%, 109%). Patients with a history of colonization with organisms associated with a more rapid decline in pulmonary status, including but not limited to Burkholderia cenocepacia, Burkholderia dolosa, or Mycobacterium abscessus, or who had an abnormal liver function test at screening (ALT, AST, ALP, or GGT ≥3 × ULN, or total bilirubin ≥2 × ULN), were excluded from the trials. Patients in Trial 5 were eligible to roll over into an open-label extension study.

In Trial 5, the primary efficacy endpoint was absolute change in ppFEV1 from baseline through week 24. Secondary efficacy endpoints were absolute change in sweat chloride through week 24, absolute change in CFQ-R respiratory domain score through week 24, absolute change in growth parameters (BMI, weight) at week 24, and number of pulmonary exacerbation events through week 24. Table 13 provides a summary of the primary and secondary efficacy results.

Table 13: Primary and Secondary Efficacy Analyses, Full Analysis Set (Trial 5)
Analysis | Statistic | Treatment Difference [Treatment difference was provided as the outcome measure for changes in ppFEV1, sweat chloride, CFQ-R RD and BMI; Rate ratio provided as the outcome measure for the number of pulmonary exacerbations.] for TRIKAFTA (N=205) vs Placebo (N=102)
Primary
Absolute change in ppFEV1 from baseline through Week 24 (percentage points) | Treatment difference (95% CI) P value | 9.2 (7.2, 11.3) P<0.0001
Secondary
Absolute change in sweat chloride from baseline through Week 24 (mmol/L) | Treatment difference (95% CI) P value | -28.3 (-32.1, -24.5) P<0.0001
Absolute change in CFQ-R respiratory domain score from baseline through Week 24 (points) | Treatment difference (95% CI) P value | 19.5 (15.5, 23.5) P<0.0001
Absolute change from baseline in BMI at Week 24 (kg/m^2) | Treatment difference (95% CI) P value | 0.47 (0.24, 0.69) P<0.0001
Absolute change from baseline in weight at Week 24 (kg) | Treatment difference (95% CI) P value | 1.3 (0.6, 1.9) P<0.0001
Number of pulmonary exacerbations through Week 24 [Number of pulmonary exacerbation events (event rate per year calculated based on 48 weeks per year) in the TRIKAFTA group were 21 (0.17) and in the placebo group were 40 (0.63).] | Rate ratio (95% CI) P value | 0.28 (0.15, 0.51) P<0.0001
BMI: body mass index; CFQ-R: Cystic Fibrosis Questionnaire-Revised; CI: confidence interval; N: total sample size; P: probability; ppFEV1: percent predicted forced expiratory volume in 1 second.

16 HOW SUPPLIED/STORAGE AND HANDLING

TRIKAFTA tablets are co-packaged blister pack sealed into a printed wallet, containing elexacaftor, tezacaftor and ivacaftor fixed-dose combination tablets and ivacaftor tablets. Four such wallets are placed in a printed outer carton. TRIKAFTA tablets are supplied as follows:

Table 14: TRIKAFTA Tablets and Package Configuration
Strengths | Tablet Description | Package Configuration | NDC
elexacaftor 50 mg, tezacaftor 25 mg, and ivacaftor 37.5 mg tablets | light orange, oblong-shaped, debossed with "T50" on one side and plain on the other | 84-count carton containing 4 wallets, each wallet containing 14 tablets of elexacaftor, tezacaftor and ivacaftor, and 7 tablets of ivacaftor | NDC 51167-106-02
Ivacaftor 75 mg | light blue, film coated, oblong-shaped, printed with the characters "V 75" in black ink on one side and plain on the other | 84-count carton containing 4 wallets, each wallet containing 14 tablets of elexacaftor, tezacaftor and ivacaftor, and 7 tablets of ivacaftor | NDC 51167-106-02
elexacaftor 100 mg, tezacaftor 50 mg, and ivacaftor 75 mg | orange, oblong-shaped, debossed with "T100" on one side and plain on the other | 84-count carton containing 4 wallets, each wallet containing 14 tablets of elexacaftor, tezacaftor and ivacaftor, and 7 tablets of ivacaftor | NDC 51167-331-01
Ivacaftor 150 mg | light blue, film-coated, oblong-shaped, printed with the characters "V 150" in black ink on one side and plain on the other | 84-count carton containing 4 wallets, each wallet containing 14 tablets of elexacaftor, tezacaftor and ivacaftor, and 7 tablets of ivacaftor | NDC 51167-331-01

TRIKAFTA oral granules are supplied in morning and evening unit-dose packets. The morning dose packets contain a fixed-dose combination of elexacaftor, tezacaftor, and ivacaftor oral granules. The evening dose packets contain ivacaftor oral granules. The packets are placed into a printed wallet. Four such wallets are placed in a printed outer carton. TRIKAFTA granules are supplied as follows:

Table 15: TRIKAFTA Oral Granules and Package Configuration
Strengths | Granule Description | Package Configuration | NDC
Elexacaftor 80 mg, tezacaftor 40 mg, and ivacaftor 60 mg | white to off-white, sweetened, unflavored granules approximately 2 mm in diameter enclosed in white and blue unit-dose packets | 56-count carton containing 4 wallets, each wallet containing 7 white and blue packets of elexacaftor, tezacaftor and ivacaftor, and 7 white and green packets of ivacaftor | NDC 51167-445-01
Ivacaftor 59.5 mg | white to off-white, sweetened, unflavored granules approximately 2 mm in diameter enclosed in white and green unit-dose packets | 56-count carton containing 4 wallets, each wallet containing 7 white and blue packets of elexacaftor, tezacaftor and ivacaftor, and 7 white and green packets of ivacaftor | NDC 51167-445-01
Elexacaftor 100 mg, tezacaftor 50 mg, and ivacaftor 75 mg | white to off-white, sweetened, unflavored granules approximately 2 mm in diameter enclosed in white and orange unit-dose packets | 56-count carton containing 4 wallets, each wallet containing 7 white and orange packets of elexacaftor, tezacaftor and ivacaftor, and 7 white and pink packets of ivacaftor | NDC 51167-446-01
Ivacaftor 75 mg | white to off-white, sweetened, unflavored granules approximately 2 mm in diameter enclosed in white and pink unit-dose packets | 56-count carton containing 4 wallets, each wallet containing 7 white and orange packets of elexacaftor, tezacaftor and ivacaftor, and 7 white and pink packets of ivacaftor | NDC 51167-446-01

STORAGE AND HANDLING

Store at 20 ºC – 25 ºC (68 ºF – 77 ºF); excursions permitted to 15 ºC – 30 ºC (59 ºF – 86 ºF) [see USP Controlled Room Temperature].

17 PATIENT COUNSELING INFORMATION

Advise the patient to read the FDA-approved patient labeling (Medication Guide).

Drug-Induced Liver Injury and Liver Failure

Inform patients that TRIKAFTA is associated with a serious risk for drug-induced liver injury and that liver injury resulting in liver failure leading to liver transplantation or death have occurred, including in patients without a history of liver disease.

Advise all patients that liver function tests (ALT, AST, alkaline phosphatase, and bilirubin) should be assessed prior to initiating TRIKAFTA and then assessed every month during the first 6 months of treatment, then every 3 months for the next 12 months, then at least annually thereafter. Inform patients with a history of liver disease or liver function test elevations at baseline that more frequent monitoring may be necessary. Instruct patients to interrupt treatment with TRIKAFTA if symptoms of liver injury occur (e.g., jaundice, right upper quadrant pain, nausea, vomiting, altered mental status, ascites) and to notify their healthcare provider immediately. [see Dosage and Administration (2.1) and Warnings and Precautions (5.1)].

Drug Interactions with CYP3A Inducers and Inhibitors

Ask patients to tell you all the medications they are taking including any herbal supplements or vitamins. Inform patients that concomitant use of TRIKAFTA with strong CYP3A inducers (e.g., rifampin, St. John's wort) is not recommended, as they may reduce the efficacy of TRIKAFTA. Dose reduction to two elexacaftor/tezacaftor/ivacaftor tablets or one elexacaftor/tezacaftor/ivacaftor oral granules packet twice a week, taken approximately 3 to 4 days apart is recommended when used concomitantly with strong CYP3A inhibitors, such as ketoconazole. Advise the patient not to take the evening dose of ivacaftor. Dose reduction to two elexacaftor/tezacaftor/ivacaftor tablets or one elexacaftor/tezacaftor/ivacaftor oral granules packet and one ivacaftor tablet or ivacaftor oral granules packet, taken on alternate days, is recommended when used concomitantly with moderate CYP3A inhibitors, such as fluconazole. Advise the patient not to take the evening dose of ivacaftor. Food or drink containing grapefruit should be avoided [see Dosage and Administration (2.4), Warnings and Precautions (5), Drug Interactions (7.1) and Clinical Pharmacology (12.3)].

Hypersensitivity Reactions, Including Anaphylaxis

Hypersensitivity reactions including angioedema and anaphylaxis are possible with use of TRIKAFTA. Inform patients of the early signs of hypersensitivity reactions including rash, hives, itching, facial swelling, tightness of the chest and wheezing. Advise patients to discontinue use of TRIKAFTA immediately and contact their physician or go to the emergency department if these symptoms occur [see Warnings and Precautions (5.2)].

Intracranial Hypertension

Inform patients that intracranial hypertension has occurred with the use of TRIKAFTA. Instruct patients to notify their healthcare provider right away if they experience signs and symptoms of intracranial hypertension, including headache, blurred vision, diplopia, and vision loss [see Warnings and Precautions (5.3)].

Cataracts

Inform patients that abnormality of the eye lens (cataract) has been noted in some children and adolescents receiving ivacaftor-containing regimens. Baseline and follow-up ophthalmological examinations should be performed in pediatric patients initiating treatment with TRIKAFTA [see Warnings and Precautions (5.6) and Use in Specific Populations (8.4)].

Administration

Inform patients that TRIKAFTA is best absorbed by the body when taken with food that contains fat. A typical CF diet will satisfy this requirement. Examples include eggs, butter, peanut butter, whole-milk dairy products (such as whole milk, cheese and yogurt), etc. [see Dosage and Administration (2.2) and Clinical Pharmacology (12.3)].

Patients should be informed about what to do in the event they miss a dose [see Dosage and Administration (2.5)] of TRIKAFTA:

- If 6 hours or less have passed since the missed morning or evening dose is usually taken, patients should be instructed to take the prescribed dose with fat-containing food as soon as possible.
- If more than 6 hours have passed since:
  - the time the morning dose is usually taken, patients should be instructed to take the morning dose as soon as possible, and not take the evening dose. Patients should take the next scheduled morning dose at the usual time.
  - the time the evening dose is usually taken, patients should be instructed to not take the missed evening dose. Patients should take the next scheduled morning dose at the usual time.
- Patients should be instructed to not take the morning and evening doses at the same time.
- Patients should be advised to contact their health care provider if they have questions.

Manufactured for
Vertex Pharmaceuticals Incorporated
50 Northern Avenue
Boston, MA 02210

TRIKAFTA, VERTEX and Vertex triangle logo are registered trademarks of Vertex Pharmaceuticals Incorporated.
All other trademarks referenced herein are the property of their respective owners.
© 2025 Vertex Pharmaceuticals Incorporated
All Rights Reserved

MEDICATION GUIDE
TRIKAFTA® (tri-KAF-tuh)
(elexacaftor, tezacaftor, and ivacaftor tablets; ivacaftor tablets), co packaged for oral use
(elexacaftor, tezacaftor, and ivacaftor oral granules; ivacaftor oral granules), co-packaged

What is the most important information I should know about TRIKAFTA?
TRIKAFTA can cause serious liver damage and liver failure. Liver failure leading to transplantation and death have been seen in some people with or without a history of liver problems taking TRIKAFTA.

Your healthcare provider will do blood tests to check your liver:

- before you start TRIKAFTA
- then every month during your first 6 months of taking TRIKAFTA
- then every 3 months during the next 12 months of taking TRIKAFTA
- then at least every year while you are taking TRIKAFTA

Your healthcare provider may do blood tests to check the liver more often if you have had high liver enzymes in your blood in the past or are experiencing signs or symptoms of liver injury.
Stop taking TRIKAFTA and call your healthcare provider right away if you have any of the following symptoms of liver problems:

- pain, swelling, or discomfort in the upper right stomach (abdominal) area
- yellowing of your skin or the white part of your eyes
- mental changes

- nausea or vomiting
- dark, amber-colored urine
- loss of appetite
- have fluid in your stomach area (ascites)

What is TRIKAFTA?

- TRIKAFTA is a prescription medicine used for the treatment of cystic fibrosis (CF) in people aged 2 years and older who have at least one copy of the F508del mutation in the cystic fibrosis transmembrane conductance regulator (CFTR) gene or another mutation that is responsive to treatment with TRIKAFTA.
- Talk to your healthcare provider to learn if you have an indicated CF gene mutation.

It is not known if TRIKAFTA is safe and effective in children under 2 years of age.

What should I tell my healthcare provider before taking TRIKAFTA?
Before taking TRIKAFTA, tell your healthcare provider about all of your medical conditions, including if you:

- have or have had liver problems.
- are allergic to TRIKAFTA or any ingredients in TRIKAFTA. See the end of this medication guide for a complete list of ingredients in TRIKAFTA.
- have kidney problems.
- are pregnant or plan to become pregnant. It is not known if TRIKAFTA will harm your unborn baby. You and your healthcare provider should decide if you will take TRIKAFTA while you are pregnant.
- are breastfeeding or planning to breastfeed. It is not known if TRIKAFTA passes into your breast milk. You and your healthcare provider should decide if you will take TRIKAFTA while you are breastfeeding.

Tell your healthcare provider about all the medicines you take, including prescription and over-the-counter medicines, vitamins, and herbal supplements.
TRIKAFTA may affect the way other medicines work and other medicines may affect how TRIKAFTA works.
The dose of TRIKAFTA may need to be adjusted when taken with certain medicines. Ask your healthcare provider or pharmacist for a list of these medicines if you are not sure.
Especially tell your healthcare provider if you take:

- antibiotics such as rifampin (RIFAMATE®, RIFATER®) or rifabutin (MYCOBUTIN®)
- seizure medicines such as phenobarbital, carbamazepine (TEGRETOL®, CARBATROL®, EQUETRO®), or phenytoin (DILANTIN®, PHENYTEK®)
- St. John's wort
- antifungal medicines including ketoconazole, itraconazole (such as SPORANOX®), posaconazole (such as NOXAFIL®), voriconazole (such as VFEND®), or fluconazole (such as DIFLUCAN®).
- antibiotics including telithromycin, clarithromycin (such as BIAXIN®), or erythromycin (such as ERY-TAB®).

Know the medicines you take. Keep a list of them to show your healthcare provider and pharmacist when you get a new medicine.

How should I take TRIKAFTA?

- Take TRIKAFTA exactly as your healthcare provider tells you to take it.
- Take TRIKAFTA by mouth only.
- TRIKAFTA consists of 2 different doses (a morning dose and an evening dose taken about 12 hours apart). Each dose has different ingredients.
- Always take TRIKAFTA oral granules or tablets with food that contains fat. Examples of fat-containing foods include butter, oil, eggs, peanut butter, nuts, meat, and whole-milk dairy products such as whole milk, cheese, and yogurt.
- TRIKAFTA oral granules (age 2 to less than 6 years weighing less than 31 pounds (14 kg)):
  - The white and blue packets each contain the medicines elexacaftor, tezacaftor, and ivacaftor. Take one morning dose packet in the morning.
  - The white and green color packets each contain the medicine ivacaftor. Take one evening dose packet in the evening.
- TRIKAFTA oral granules (age 2 to less than 6 years weighing 31 pounds (14 kg) or more):
  - The white and orange packets each contain the medicines elexacaftor, tezacaftor, and ivacaftor. Take one morning dose packet in the morning.
  - The white and pink color packets each contain the medicine ivacaftor. Take one evening dose packet in the evening.
- To prepare TRIKAFTA oral granules:
  - Hold the packet with the cut line on top.
  - Shake the packet gently to settle the TRIKAFTA oral granules.
  - Tear or cut the packet open along the cut line.
  - Carefully pour all the TRIKAFTA oral granules in the packet into 1 teaspoon (5 mL) of soft food or liquid in a small container (like an empty bowl). The food or liquid should be at or below room temperature. Some examples of soft foods or liquids include pureed fruits or vegetables, yogurt, applesauce, water, milk, or juice.
  - Mix the TRIKAFTA granules with food or liquid.
  - After mixing, give TRIKAFTA within 1 hour. Make sure all the medicine is taken.
- TRIKAFTA tablets (age 6 to less than 12 years weighing less than 66 pounds (30 kg)):
  - The light orange tablet is marked with 'T50' and each tablet contains the medicines elexacaftor, tezacaftor and ivacaftor. Take 2 light orange tablets in the morning.
  - The light blue tablet is marked with 'V 75' and contains the medicine ivacaftor. Take 1 light blue tablet in the evening.
- TRIKAFTA tablets (age 6 to less than 12 years weighing 66 pounds (30 kg) or more, and age 12 years and older):
  - The orange tablet is marked with 'T100' and each tablet contains the medicines elexacaftor, tezacaftor and ivacaftor. Take 2 orange tablets in the morning.
  - The light blue tablet is marked with 'V 150' and contains the medicine ivacaftor. Take 1 light blue tablet in the evening.
- Take TRIKAFTA tablets whole.
- If you miss a dose of TRIKAFTA and:
  - it is 6 hours or less from the time you usually take the morning dose or the evening dose, take the missed dose with food that contains fat as soon as you can. Then take your next dose at your usual time.
  - it is more than 6 hours from the time you usually take the morning dose, take the missed dose with food that contains fat as soon as you can. Do not take the evening dose.
  - it is more than 6 hours from the time you usually take the evening dose, do not take the missed dose. Take your next morning dose at the usual time with food that contains fat.
  - Do not take more than your usual dose of TRIKAFTA to make up for a missed dose.
  - Do not take the morning and evening doses at the same time.
- If you have liver problems, your healthcare provider may tell you to take TRIKAFTA differently.

If you are not sure about your dosing, call your healthcare provider.

What should I avoid while taking TRIKAFTA?
Avoid food or drink that contains grapefruit while you are taking TRIKAFTA.

What are the possible or reasonably likely side effects of TRIKAFTA?
TRIKAFTA can cause serious side effects, including:

- See "What is the most important information I should know about TRIKAFTA?"
- Serious Allergic Reactions can happen to people who are treated with TRIKAFTA. Call your healthcare provider or go to the emergency room right away if you have any symptoms of an allergic reaction. Symptoms of an allergic reaction may include:
  - rash or hives
  - tightness of the chest or throat or difficulty breathing
  - swelling of the face, lips and/or tongue, difficulty swallowing
  - light-headedness or dizziness
- Increased pressure around the brain (intracranial hypertension) has happened in people treated with TRIKAFTA. If you experience an unusual headache, blurred vision, double vision, or vision loss, call your healthcare provider right away.
- Abnormality of the eye lens (cataract) has happened in some children and adolescents treated with TRIKAFTA. If you are a child or adolescent, your healthcare provider should perform eye examinations before and during treatment with TRIKAFTA to look for cataracts.

The most common side effects of TRIKAFTA include:

- headache
- upper respiratory tract infection (common cold) including stuffy and runny nose
- stomach (abdominal) pain
- diarrhea
- rash

- increase in liver enzymes
- increase in a certain blood enzyme called creatine phosphokinase
- flu (influenza)
- inflamed sinuses
- increase in blood bilirubin
- constipation

Tell your healthcare provider if you have any side effect that bothers you or that does not go away.
These are not all the possible side effects of TRIKAFTA. For more information, ask your healthcare provider or pharmacist.
Call your doctor for medical advice about side effects. You may report side effects to FDA at 1-800-FDA-1088.

How should I store TRIKAFTA?

- Store TRIKAFTA at room temperature between 68ºF to 77ºF (20ºC to 25ºC).

Keep TRIKAFTA and all medicines out of the reach of children.

General information about the safe and effective use of TRIKAFTA.
Medicines are sometimes prescribed for purposes other than those listed in a Medication Guide. Do not use TRIKAFTA for a condition for which it was not prescribed. Do not give TRIKAFTA to other people, even if they have the same symptoms that you have. It may harm them.
You can ask your pharmacist or healthcare provider for information about TRIKAFTA that is written for health professionals.

What are the ingredients in TRIKAFTA?
Elexacaftor/tezacaftor/ivacaftor tablets:
Active ingredients: elexacaftor, tezacaftor and ivacaftor.
Inactive ingredients: croscarmellose sodium, hypromellose, hypromellose acetate succinate, magnesium stearate, microcrystalline cellulose, sodium lauryl sulfate. The tablet film coat contains hydroxypropyl cellulose, hypromellose, iron oxide red, iron oxide yellow, talc, and titanium dioxide.
Ivacaftor tablets:
Active ingredients: ivacaftor.
Inactive ingredients: colloidal silicon dioxide, croscarmellose sodium, hypromellose acetate succinate, lactose monohydrate, magnesium stearate, microcrystalline cellulose, and sodium lauryl sulfate.
The tablet film coat contains carnauba wax, FD&C Blue #2, PEG 3350, polyvinyl alcohol, talc, and titanium oxide.
The printing ink contains ammonium hydroxide, iron oxide black, propylene glycol, and shellac.
Elexacaftor/tezacaftor/ivacaftor oral granules:
Active ingredients: elexacaftor, tezacaftor, and ivacaftor.
Inactive ingredients: colloidal silicon dioxide, croscarmellose sodium, hypromellose, hypromellose acetate succinate, lactose monohydrate, magnesium stearate, mannitol, sodium lauryl sulfate, and sucralose.
Ivacaftor oral granules:
Active ingredients: ivacaftor.
Inactive ingredients: colloidal silicon dioxide, croscarmellose sodium, hypromellose acetate succinate, lactose monohydrate, magnesium stearate, mannitol, sodium lauryl sulfate, and sucralose.
Manufactured for: Vertex Pharmaceuticals Incorporated; 50 Northern Avenue, Boston, MA 02210
TRIKAFTA, VERTEX and associated logos are registered trademarks of Vertex Pharmaceuticals Incorporated.
All other trademarks referenced herein are the property of their respective owners.
©2025 Vertex Pharmaceuticals Incorporated
For more information, go to www.trikafta.com or call 1-877-752-5933.

This Medication Guide has been approved by the U.S. Food and Drug Administration.

Revised: 09/2025

PRINCIPAL DISPLAY PANEL - Kit Carton

NDC 51167-331-01
Rx Only

trikafta®
(elexacaftor, tezacaftor and ivacaftor)
100 mg, 50 mg and 75 mg;
(ivacaftor) 150 mg tablets

ATTENTION PHARMACIST: Dispense enclosed
Medication Guide to each patient.

84 Tablets
4-wallets (each containing 14 tablets of elexacaftor, tezacaftor,
and ivacaftor and 7 tablets of ivacaftor)

LIFT HERE TO OPEN ►

PRINCIPAL DISPLAY PANEL - Kit Carton - 51167-106-02

NDC 51167-106-02
Rx Only

trikafta®
(elexacaftor, tezacaftor and ivacaftor)
50 mg, 25 mg and 37.5 mg;
(ivacaftor) 75 mg tablets

ATTENTION PHARMACIST: Dispense enclosed
Medication Guide to each patient.

84 Tablets
4-wallets (each containing 14 tablets of elexacaftor, tezacaftor,
and ivacaftor and 7 tablets of ivacaftor)

LIFT HERE TO OPEN →

PRINCIPAL DISPLAY PANEL - Kit Carton - 51167-445-01

NDC 51167-445-01
Rx only

trikafta®
(elexacaftor, tezacaftor, ivacaftor) oral granules
80 mg/40 mg/60 mg
Co-packaged with
(ivacaftor) oral granules
59.5 mg

80 mg
40 mg
60 mg
and
59.5 mg

56 packets
Carton contains: 4 individual
wallets with 14 packets per wallet

ATTENTION PHARMACIST: Dispense enclosed Medication Guide to each patient.

Lift here to open

PRINCIPAL DISPLAY PANEL - Kit Carton - 51167-446-01

NDC 51167-446-01
Rx only

trikafta®
(elexacaftor, tezacaftor, ivacaftor) oral granules
100 mg/50 mg/75 mg
Co-packaged with
(ivacaftor) oral granules
75 mg

100 mg
50 mg
75 mg
and
75 mg

56 packets
Carton contains: 4 individual
wallets with 14 packets per wallet

ATTENTION PHARMACIST: Dispense enclosed Medication Guide to each patient.

Lift here to open